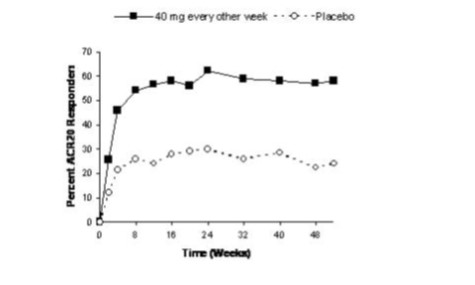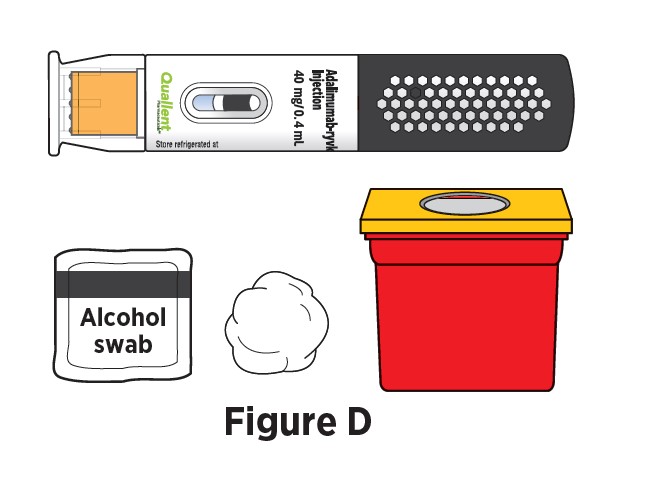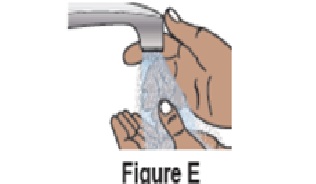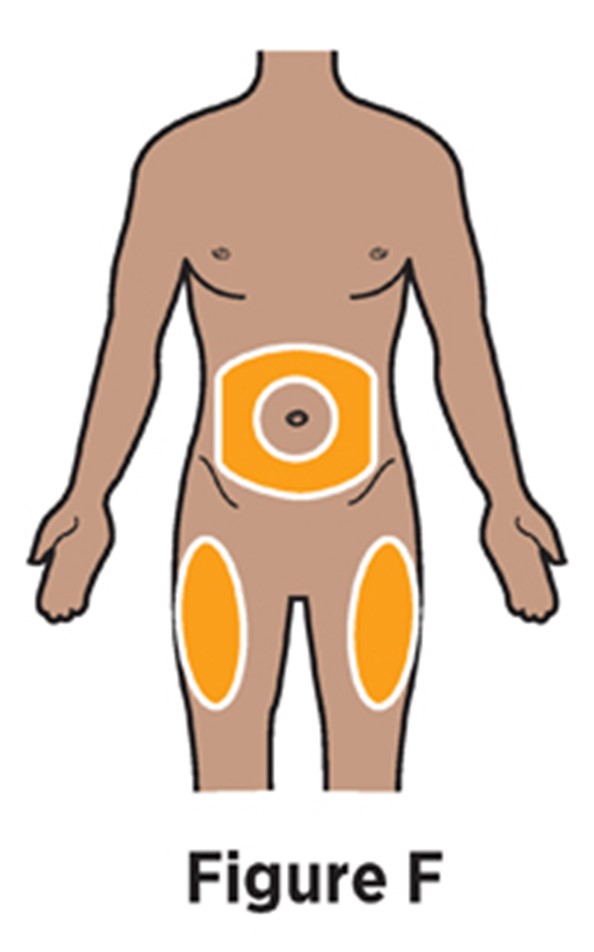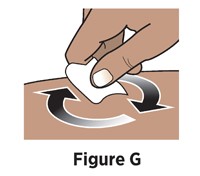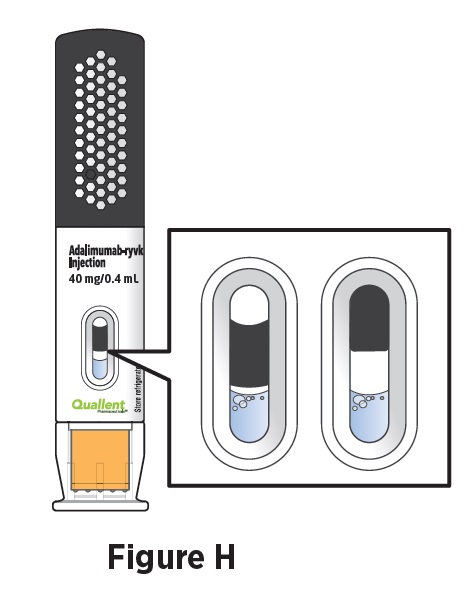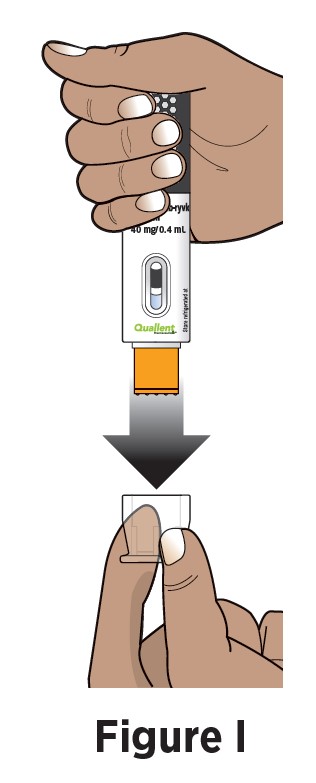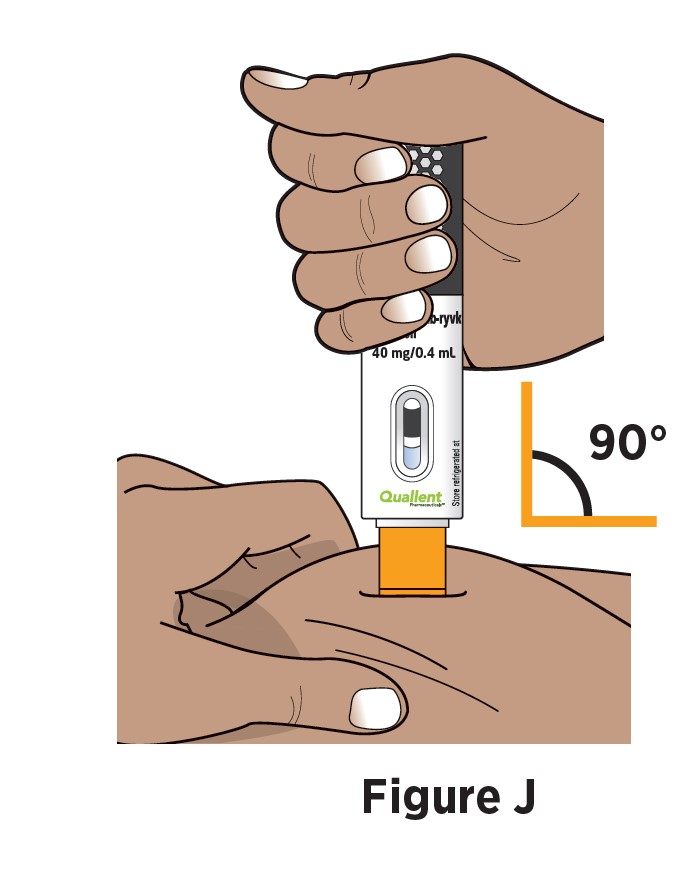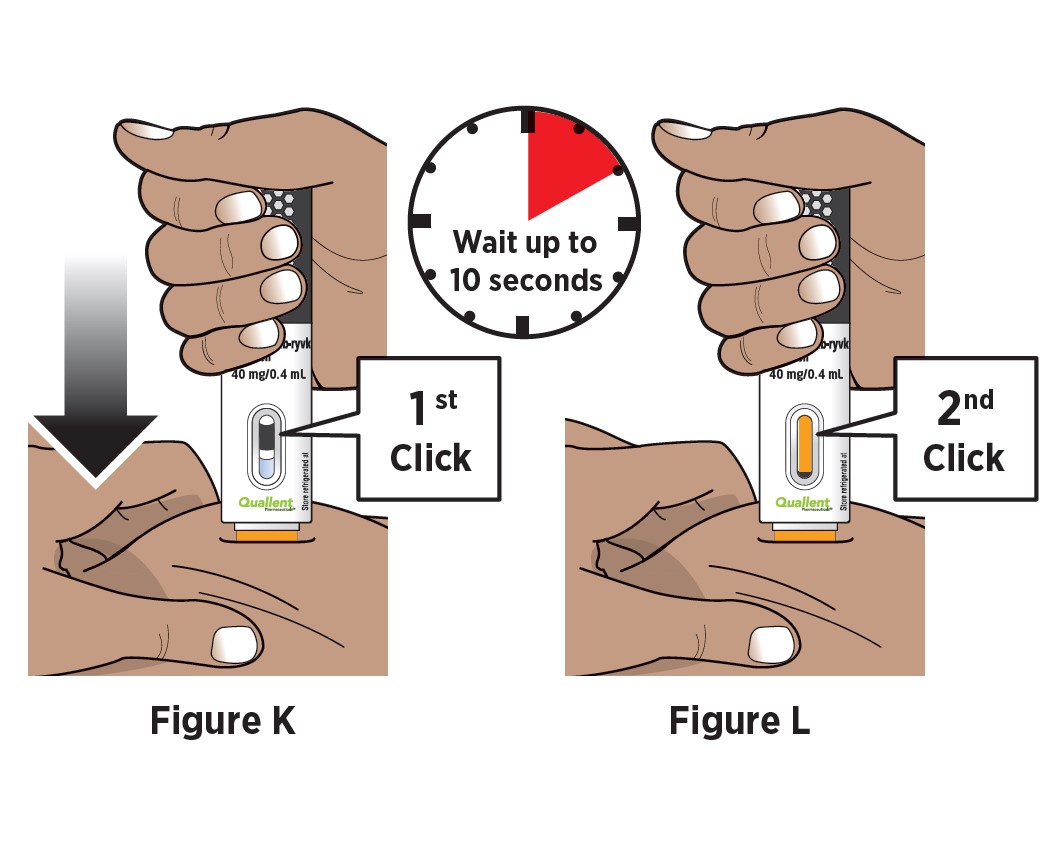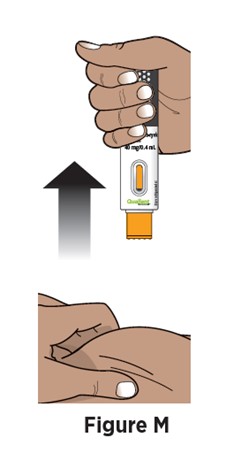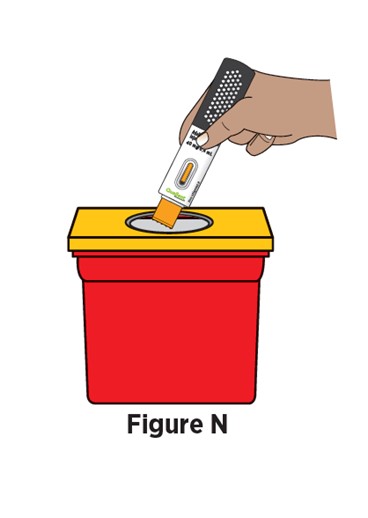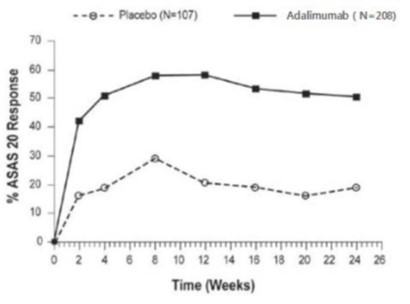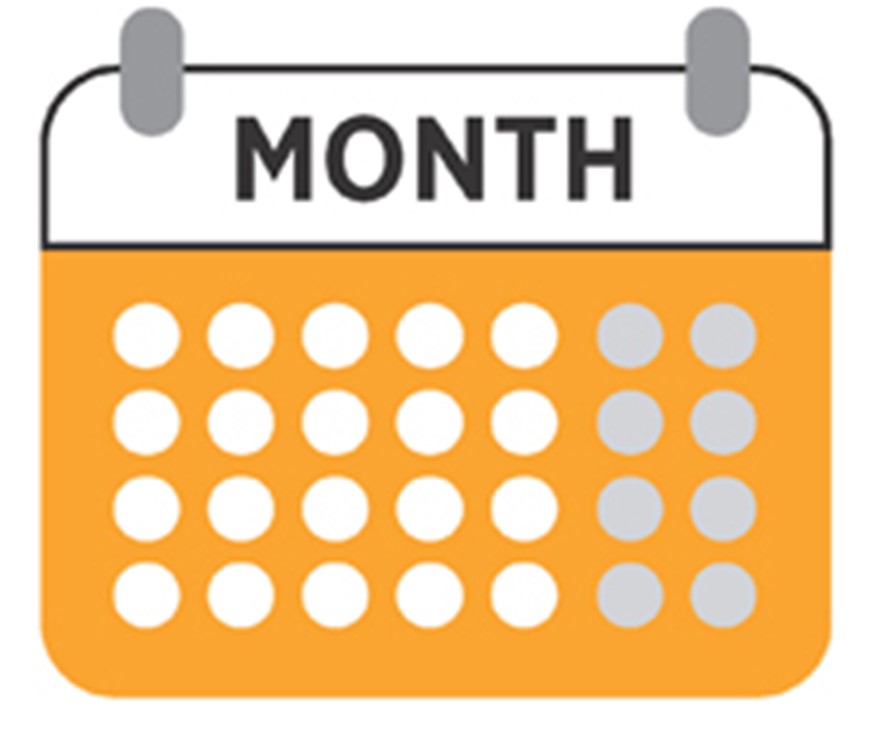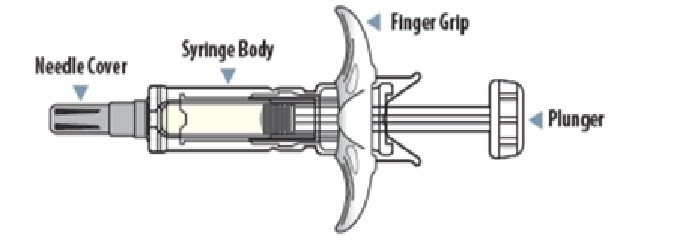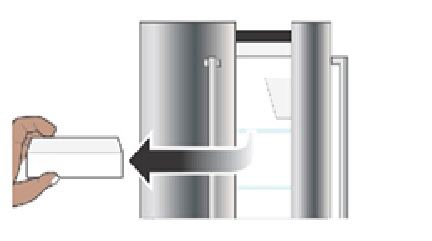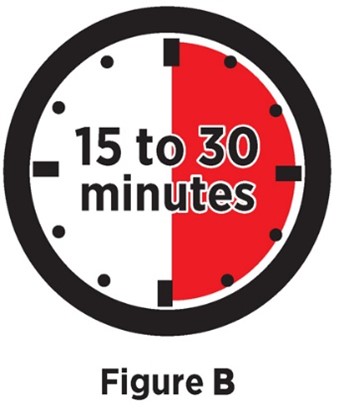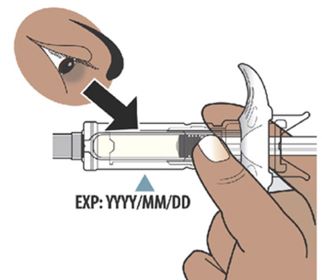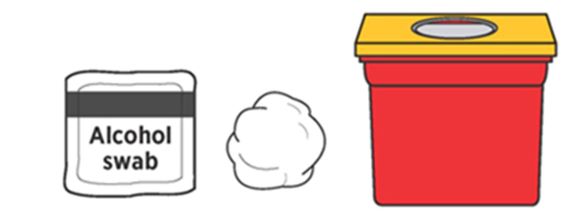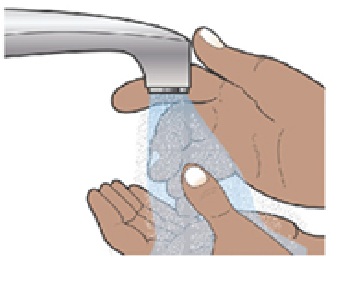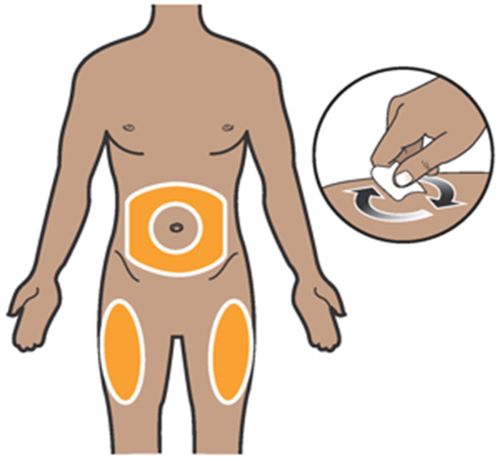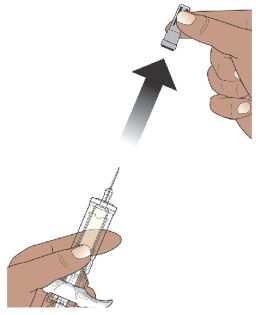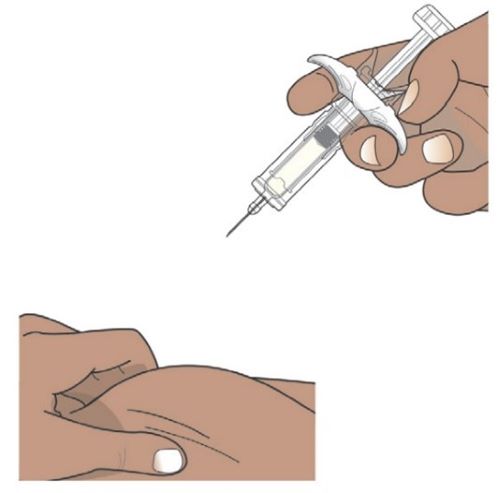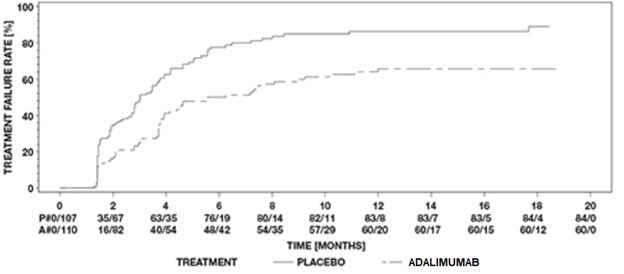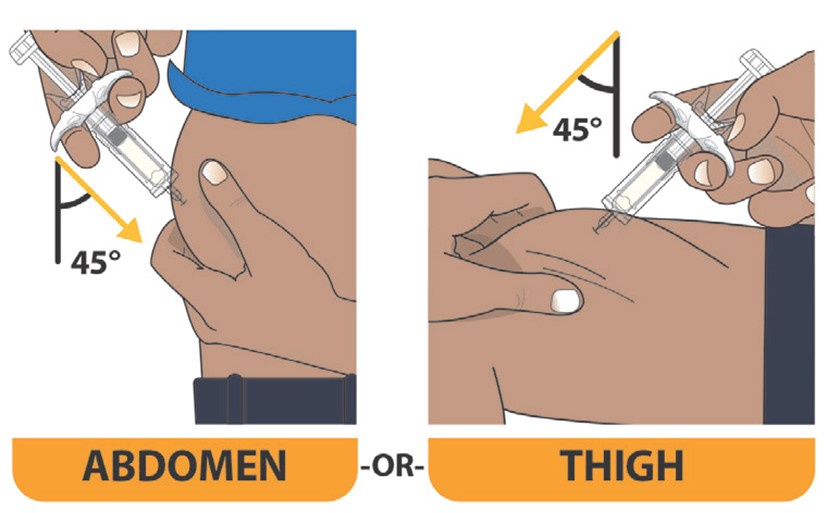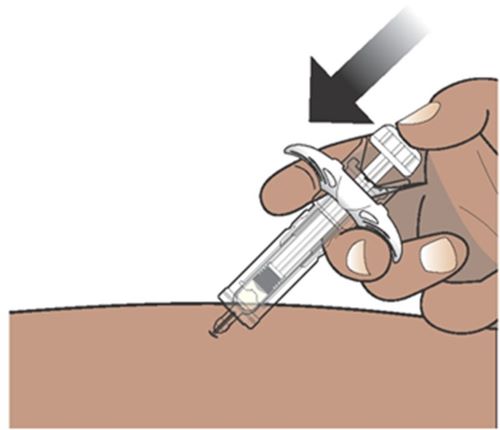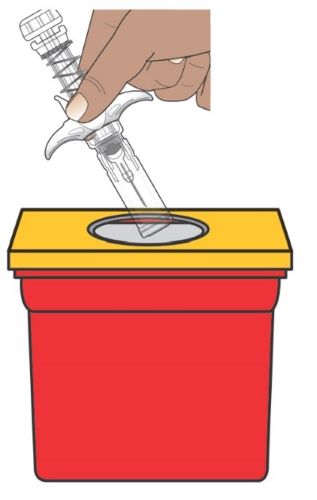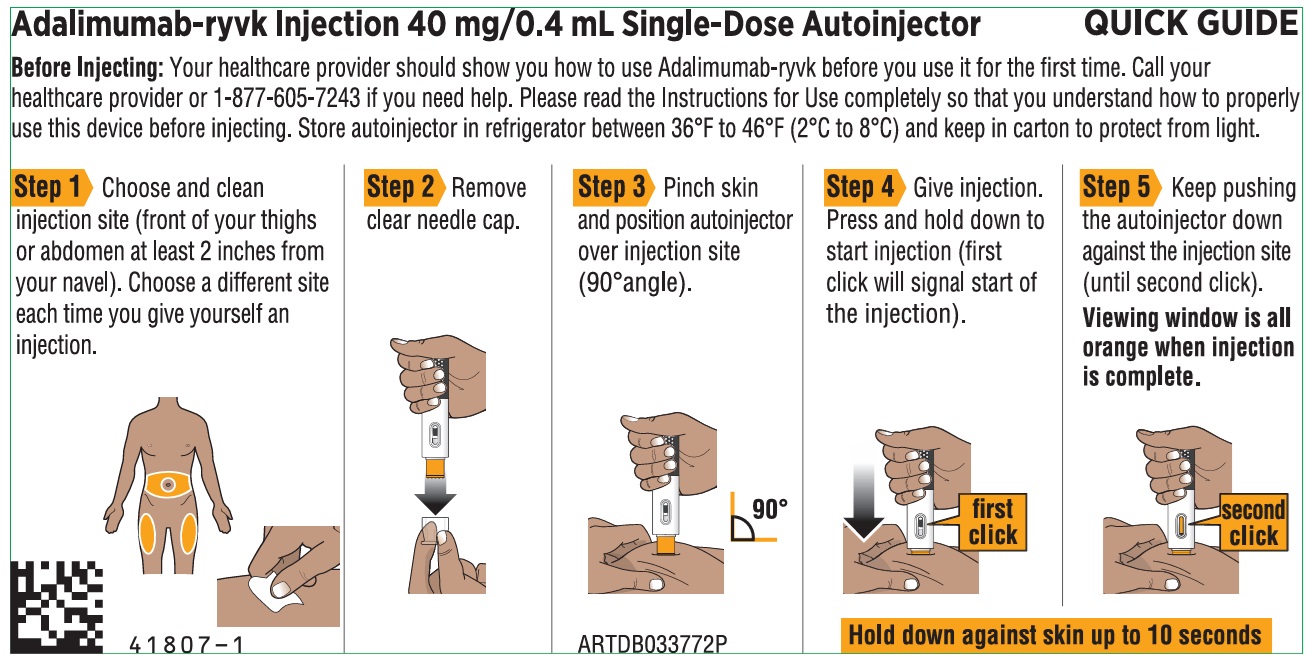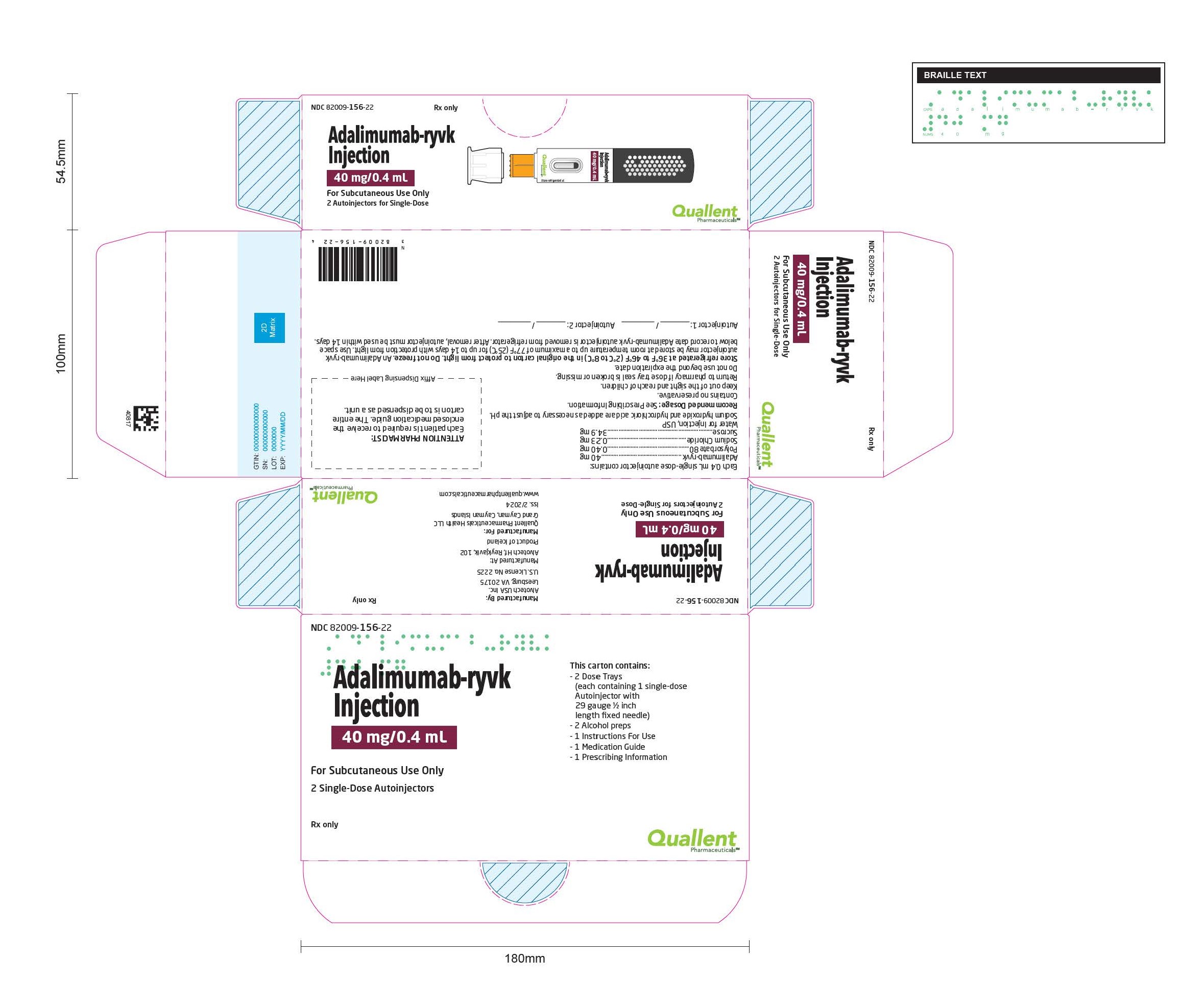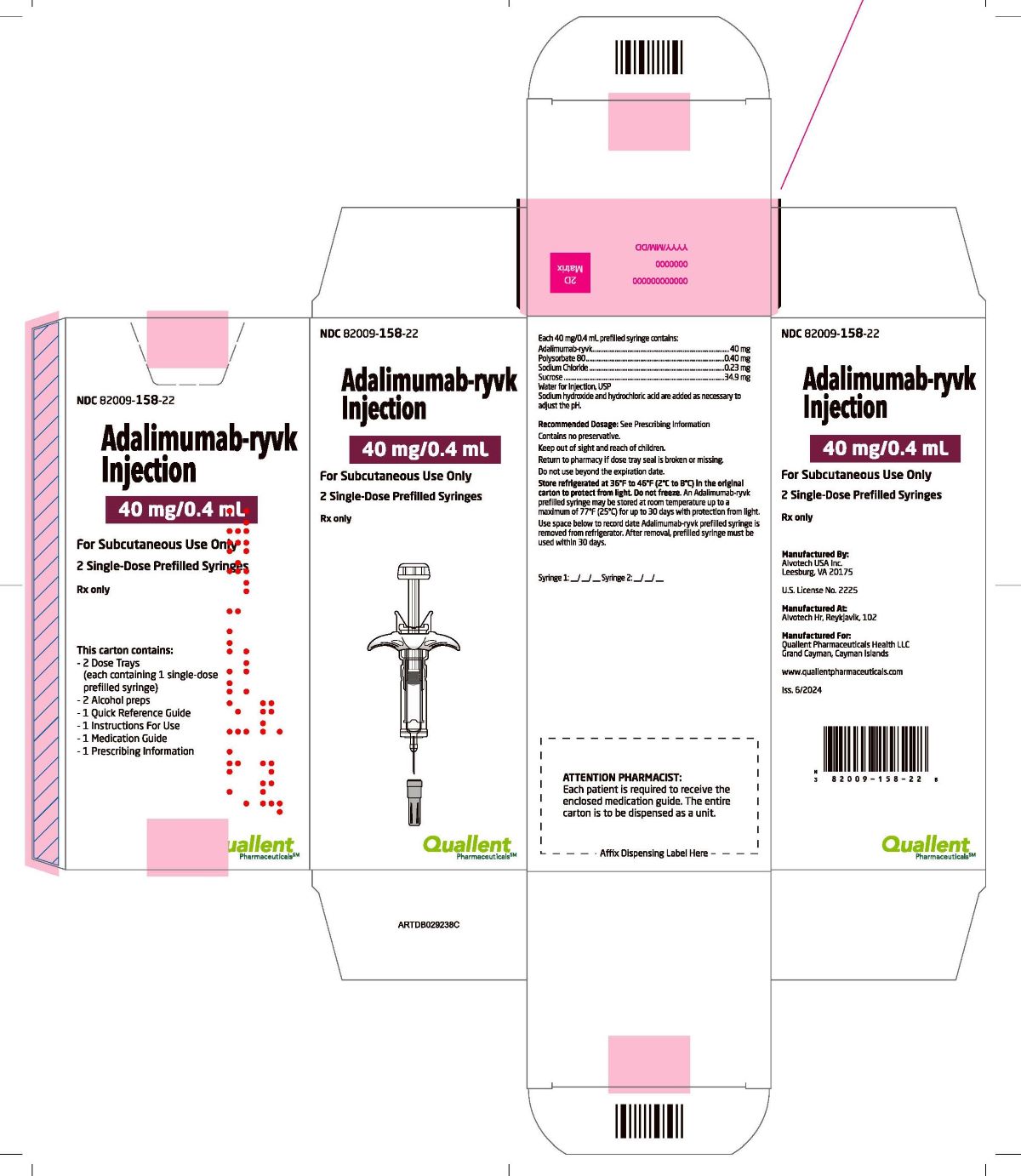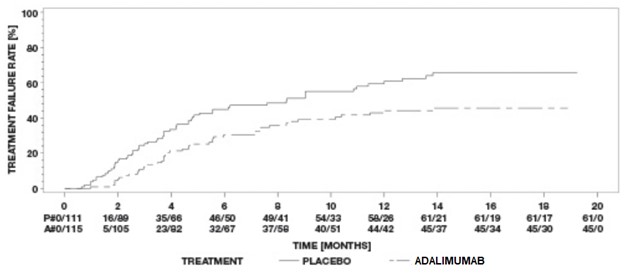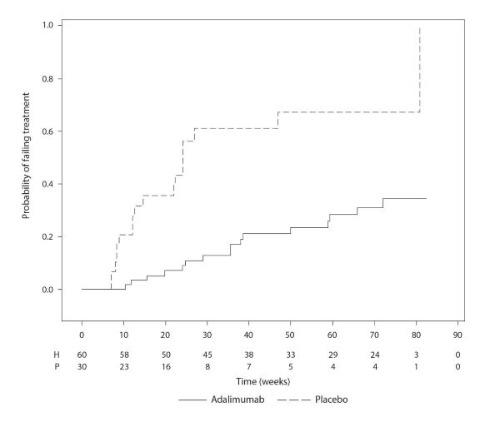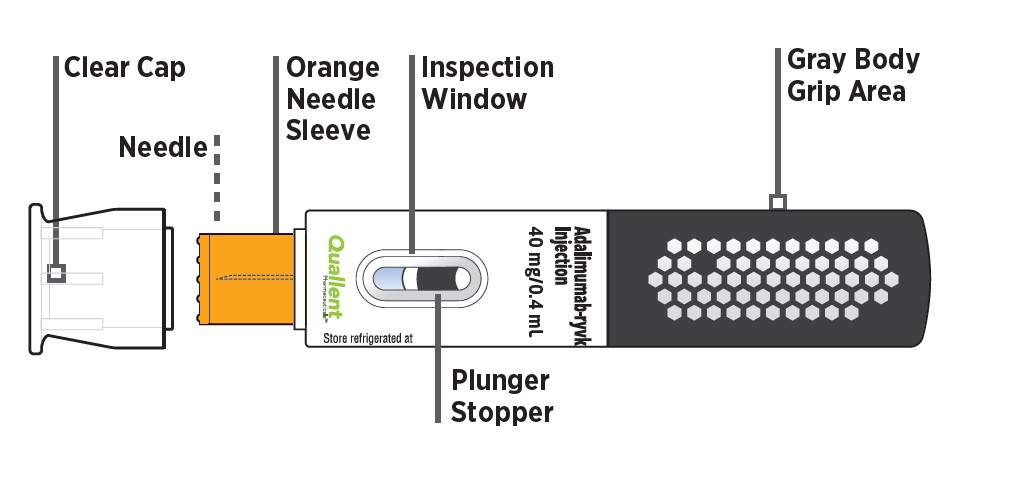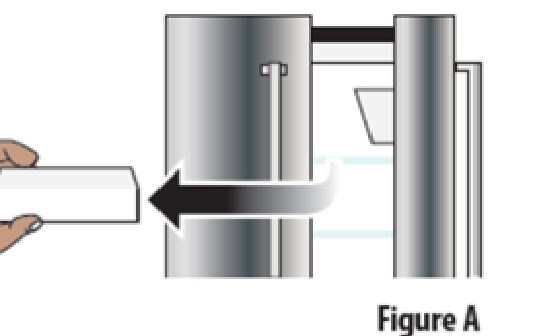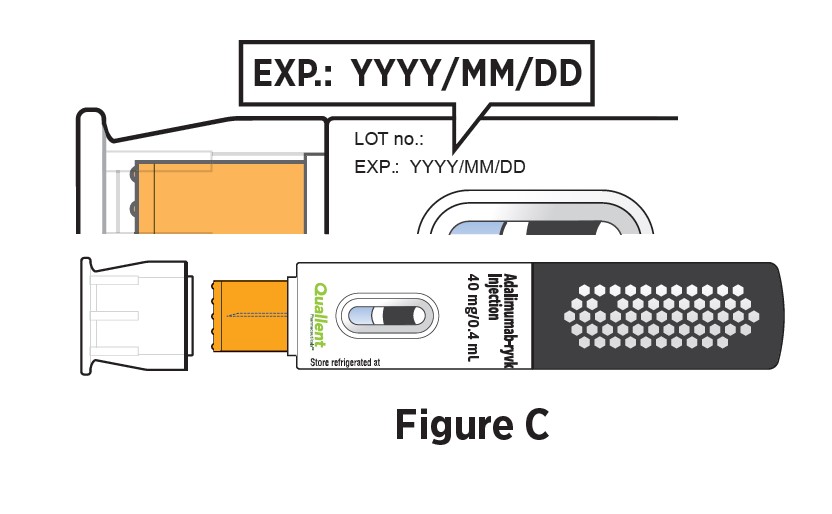 DRUG LABEL: Adalimumab-ryvk
NDC: 82009-156 | Form: KIT | Route: SUBCUTANEOUS
Manufacturer: Quallent Pharmaceuticals Health LLC
Category: prescription | Type: HUMAN PRESCRIPTION DRUG LABEL
Date: 20260119

ACTIVE INGREDIENTS: ADALIMUMAB-RYVK 40 mg/0.4 mL; ISOPROPYL ALCOHOL 0.7 mL/1 mL
INACTIVE INGREDIENTS: POLYSORBATE 80; SODIUM CHLORIDE; SUCROSE; WATER; HYDROCHLORIC ACID; SODIUM HYDROXIDE; WATER

HIGHLIGHTS OF PRESCRIBING INFORMATION

These highlights do not include all the information needed to use ADALIMUMAB-RYVK safely and effectively. See full prescribing information for ADALIMUMAB-RYVK.
ADALIMUMAB-RYVK injection, for subcutaneous use
Initial U.S. Approval: 2024
Adalimumab-ryvk is biosimilar [Biosimilar means that the biological product is approved based on data demonstrating that it is highly similar to an FDA-approved biological product, known as a reference product, and that there are no clinically meaningful differences between the biosimilar product and the reference product. Biosimilarity of Adalimumab-ryvk has been demonstrated for the condition(s) of use (e.g., indication(s), dosing regimen(s)), strength(s), dosage form(s), and route(s) of administration described in its Full Prescribing Information.] to HUMIRA® (adalimumab).

RECENT MAJOR CHANGES

Indications and Usage, Hidradenitis Suppurativa (1.8) 10/2025

Indications and Usage, Uveitis (1.9) 10/2025

Dosage and Administration, Recommended Dosage in Juvenile Idiopathic Arthritis or Pediatric Uveitis (2.3) 10/2025

Dosage and Administration, Recommended Dosage in Hidradenitis Suppurativa (2.7) 10/2025

Warnings and Precautions, Autoimmunity (5.9) 10/2025

WARNING: SERIOUS INFECTIONS and MALIGNANCY

See full prescribing information for complete boxed warning.

SERIOUS INFECTIONS (5.1, 6.1):

- Increased risk of serious infections leading to hospitalization or death, including tuberculosis (TB), bacterial sepsis, invasive fungal infections (such as histoplasmosis), and infections due to other opportunistic pathogens.
- Discontinue Adalimumab-ryvk if a patient develops a serious infection or sepsis during treatment.
- Perform test for latent TB; if positive, start treatment for TB prior to starting Adalimumab-ryvk.
- Monitor all patients for active TB during treatment, even if initial latent TB test is negative.

MALIGNANCY (5.2):

- Lymphoma and other malignancies, some fatal, have been reported in children and adolescent patients treated with TNF blockers including adalimumab products.
- Post-marketing cases of hepatosplenic T-cell lymphoma (HSTCL), a rare type of T-cell lymphoma, have occurred in adolescent and young adults with inflammatory bowel disease treated with TNF blockers including adalimumab products.

1 INDICATIONS AND USAGE

Adalimumab-ryvk is a tumor necrosis factor (TNF) blocker indicated for:

- Reducing signs and symptoms, inducing major clinical response, inhibiting the progression of structural damage, and improving physical function in adult patients with moderately to severely active rheumatoid arthritis. (1.1)
- Reducing signs and symptoms of moderately to severely active polyarticular juvenile idiopathic arthritis in patients 2 years of age and older. (1.2)
- Reducing signs and symptoms, inhibiting the progression of structural damage, and improving physical function in adult patients with active psoriatic arthritis. (1.3)
- Reducing signs and symptoms in adult patients with active ankylosing spondylitis. (1.4)
- Treatment of moderately to severely active Crohn’s disease in adults and pediatric patients 6 years of age and older. (1.5)
- Treatment of moderately to severely active ulcerative colitis in adult patients. (1.6)
  Limitations of Use: Effectiveness has not been established in patients who have lost response to or were intolerant to TNF blockers.
- Treatment of adult patients with moderate to severe chronic plaque psoriasis who are candidates for systemic therapy or phototherapy, and when other systemic therapies are medically less appropriate. (1.7)
- Treatment of moderate to severe hidradenitis suppurativa in patients 12 years of age and older (1.8)
- Treatment of non-infectious intermediate, posterior, and panuveitis in adults and pediatric patients 2 years of age and older (1.9)

2 DOSAGE AND ADMINISTRATION

- Administer by subcutaneous injection. (2)

Rheumatoid Arthritis, Psoriatic Arthritis, Ankylosing Spondylitis (2.2):

- Adults: 40 mg every other week.
  - Some patients with RA not receiving methotrexate may benefit from increasing the dosage to 40 mg every week or 80 mg every other week.

Juvenile Idiopathic Arthritis or Pediatric Uveitis (2.3):

Pediatric Weight 2 Years of Age and Older | Recommended Dosage
15 kg (33 lbs) to less than 30 kg (66 lbs) | 20 mg every other week
30 kg (66 lbs) and greater | 40 mg every other week

Crohn's Disease (2.4):

- Adults: 160 mg on Day 1 (given in one day or split over two consecutive days), 80 mg on Day 15, and 40 mg every other week starting on Day 29.
- Pediatric Patients 6 Years of Age and Older:

Pediatric Weight | Recommended Dosage
Pediatric Weight | Days 1 and 15 | Starting on Day 29
17 kg (37 lbs) to less than 40 kg (88 lbs) | Day 1: 80 mg; Day 15: 40 mg | 20 mg every other week
40 kg (88 lbs); and greater | Day 1: 160 mg (single dose or split over two consecutive days); Day 15: 80 mg | 40 mg every other week

Ulcerative Colitis (2.5):

- Adults: 160 mg on Day 1 (given in one day or split over two consecutive days), 80 mg on Day 15, and 40 mg every other week starting on Day 29.

Discontinue in patients without evidence of clinical remission by eight weeks (Day 57).

Plaque Psoriasis or Adult Uveitis (2.6):

- Adults: 80 mg initial dose, followed by 40 mg every other week starting one week after initial dose.

Hidradenitis Suppurativa (2.7):

- Adults:
  - Day 1: 160 mg (given in one day or split over two consecutive days)
  - Day 15: 80 mg
  - Day 29 and subsequent doses: 40 mg every week or 80 mg every other week
- Adolescents 12 years of age and older:

Adolescent Weight | Recommended Dosage
30 kg (66 lbs) to less than 60 kg (132 lbs) | Day 1: 80 mg; Day 8 and subsequent doses: 40 mg every other week
60 kg (132 lbs) and greater | Day 1: 160 mg (given in one day or split over two consecutive days); Day 15: 80 mg; Day 29 and subsequent doses: 40 mg every week or 80 mg every other week

3 DOSAGE FORMS AND STRENGTHS

Injection:

- Single-dose autoinjector: 80 mg/0.8 mL, and 40 mg/0.4 mL (3)
- Single-dose prefilled glass syringe: 80 mg/0.8 mL, 40 mg/0.4 mL, 20 mg/0.2 mL (3)

4 CONTRAINDICATIONS

None (4)

5 WARNINGS AND PRECAUTIONS

- Serious infections: Do not start Adalimumab-ryvk during an active infection. If an infection develops, monitor carefully, and stop Adalimumab-ryvk if infection becomes serious. (5.1)
- Invasive fungal infections: For patients who develop a systemic illness on Adalimumab-ryvk, consider empiric antifungal therapy for those who reside or travel to regions where mycoses are endemic. (5.1)
- Malignancies: Incidence of malignancies was greater in adalimumab-treated patients than in controls. (5.2)
- Anaphylaxis or serious hypersensitivity reactions may occur. (5.3)
- Hepatitis B virus reactivation: Monitor HBV carriers during and several months after therapy. If reactivation occurs, stop Adalimumab-ryvk and begin anti-viral therapy. (5.4)
- Demyelinating disease: Exacerbation or new onset, may occur. (5.5)
- Cytopenias, pancytopenia: Advise patients to seek immediate medical attention if symptoms develop, and consider stopping Adalimumab-ryvk. (5.6)
- Heart failure: Worsening or new onset, may occur. (5.8)
- Autoimmunity: Stop Adalimumab-ryvk if lupus-like syndrome or autoimmune hepatitis develop. (5.9)

6 ADVERSE REACTIONS

Most common adverse reactions (>10%) are: infections (e.g. upper respiratory, sinusitis), injection site reactions, headache and rash. (6.1)
To report SUSPECTED ADVERSE REACTIONS, contact Quallent Pharmaceuticals Health LLC at 1-877-605-7243 or FDA at 1-800-FDA-1088 or www.fda.gov/medwatch.

7 DRUG INTERACTIONS

- Abatacept: Increased risk of serious infection. (5.1, 5.11, 7.2)
- Anakinra: Increased risk of serious infection. (5.1, 5.7, 7.2)
- Live vaccines: Avoid use with Adalimumab-ryvk. (5.10, 7.3)

FULL PRESCRIBING INFORMATION

RECENT MAJOR CHANGES

Indications and Usage, Hidradenitis Suppurativa (1.8) 10/2025

Indications and Usage, Uveitis (1.9) 10/2025

Dosage and Administration, Recommended Dosage in Juvenile Idiopathic Arthritis or Pediatric Uveitis (2.3) 10/2025

Dosage and Administration, Recommended Dosage in Hidradenitis Suppurativa (2.6) 10/2025

Warnings and Precautions, Autoimmunity (5.9) 10/2025

WARNING: SERIOUS INFECTIONS and MALIGNANCY

SERIOUS INFECTIONS

Patients treated with adalimumab products, including Adalimumab-ryvk, are at increased risk for developing serious infections that may lead to hospitalization or death [see Warnings and Precautions (5.1)]. Most patients who developed these infections were taking concomitant immunosuppressants such as methotrexate or corticosteroids.

Discontinue Adalimumab-ryvk if a patient develops a serious infection or sepsis.

Reported infections include:

- Active tuberculosis (TB), including reactivation of latent TB. Patients with TB have frequently presented with disseminated or extrapulmonary disease. Test patients for latent TB before Adalimumab-ryvk use and during therapy. Initiate treatment for latent TB prior to Adalimumab-ryvk use.
- Invasive fungal infections, including histoplasmosis, coccidioidomycosis, candidiasis, aspergillosis, blastomycosis, and pneumocystosis. Patients with histoplasmosis or other invasive fungal infections may present with disseminated, rather than localized, disease. Antigen and antibody testing for histoplasmosis may be negative in some patients with active infection. Consider empiric anti-fungal therapy in patients at risk for invasive fungal infections who develop severe systemic illness.
- Bacterial, viral and other infections due to opportunistic pathogens, including Legionella and Listeria.

Carefully consider the risks and benefits of treatment with Adalimumab-ryvk prior to initiating therapy in patients with chronic or recurrent infection.

Monitor patients closely for the development of signs and symptoms of infection during and after treatment with Adalimumab-ryvk, including the possible development of TB in patients who tested negative for latent TB infection prior to initiating therapy [see Warnings and Precautions (5.1) and Adverse Reactions (6.1)].

MALIGNANCY

Lymphoma and other malignancies, some fatal, have been reported in children and adolescent patients treated with TNF blockers including adalimumab products [see Warnings and Precautions (5.2)]. Post-marketing cases of hepatosplenic T-cell lymphoma (HSTCL), a rare type of T-cell lymphoma, have been reported in patients treated with TNF blockers including adalimumab products. These cases have had a very aggressive disease course and have been fatal. The majority of reported TNF blocker cases have occurred in patients with Crohn's disease or ulcerative colitis and the majority were in adolescent and young adult males. Almost all these patients had received treatment with azathioprine or 6-mercaptopurine (6-MP) concomitantly with a TNF blocker at or prior to diagnosis. It is uncertain whether the occurrence of HSTCL is related to use of a TNF blocker or a TNF blocker in combination with these other immunosuppressants [see Warnings and Precautions (5.2)].

1 INDICATIONS AND USAGE

1.1 Rheumatoid Arthritis

Adalimumab-ryvk is indicated for reducing signs and symptoms, inducing major clinical response, inhibiting the progression of structural damage, and improving physical function in adult patients with moderately to severely active rheumatoid arthritis. Adalimumab-ryvk can be used alone or in combination with methotrexate or other non-biologic disease-modifying anti-rheumatic drugs (DMARDs).

1.2 Juvenile Idiopathic Arthritis

Adalimumab-ryvk is indicated for reducing signs and symptoms of moderately to severely active polyarticular juvenile idiopathic arthritis in patients 2 years of age and older. Adalimumab-ryvk can be used alone or in combination with methotrexate.

1.3 Psoriatic Arthritis

Adalimumab-ryvk is indicated for reducing signs and symptoms, inhibiting the progression of structural damage, and improving physical function in adult patients with active psoriatic arthritis. Adalimumab-ryvk can be used alone or in combination with non-biologic DMARDs.

1.4 Ankylosing Spondylitis

Adalimumab-ryvk is indicated for reducing signs and symptoms in adult patients with active ankylosing spondylitis.

1.5 Crohn’s Disease

Adalimumab-ryvk is indicated for the treatment of moderately to severely active Crohn’s disease in adults and pediatric patients 6 years of age and older.

1.6 Ulcerative Colitis

Adalimumab-ryvk is indicated for the treatment of moderately to severely active ulcerative colitis in adult patients.

Limitations of Use

The effectiveness of adalimumab products has not been established in patients who have lost response to or were intolerant to TNF blockers [see Clinical Studies (14.7)].

1.7 Plaque Psoriasis

Adalimumab-ryvk is indicated for the treatment of adult patients with moderate to severe chronic plaque psoriasis who are candidates for systemic therapy or phototherapy, and when other systemic therapies are medically less appropriate. Adalimumab-ryvk should only be administered to patients who will be closely monitored and have regular follow-up visits with a physician [see Warnings and Precautions (5)].

1.8 Hidradenitis Suppurativa

Adalimumab-ryvk is indicated for the treatment of moderate to severe hidradenitis suppurativa in patients 12 years of age and older.

1.9 Uveitis

Adalimumab-ryvk is indicated for the treatment of non-infectious intermediate, posterior, and panuveitis in adults and pediatric patients 2 years of age and older.

2 DOSAGE AND ADMINISTRATION

2.1 Recommended Tuberculosis Evaluation

Prior to initiating Adalimumab-ryvk and periodically during therapy, evaluate patients for active tuberculosis and test for latent infection [see Warnings and Precautions (5.1)].

2.2 Recommended Dosage in Rheumatoid Arthritis, Psoriatic Arthritis, and Ankylosing Spondylitis

The recommended subcutaneous dosage of Adalimumab-ryvk for adult patients with rheumatoid arthritis (RA), psoriatic arthritis (PsA), or ankylosing spondylitis (AS) [see Indication and Usage (1.1, 1.3, 1.4)] is 40 mg administered every other week. Methotrexate (MTX), other non-biologic DMARDS, glucocorticoids, nonsteroidal anti-inflammatory drugs (NSAIDs), and/or analgesics may be continued during treatment with Adalimumab-ryvk. In the treatment of RA, some patients not taking concomitant MTX may derive additional benefit from increasing the dosage of Adalimumab-ryvk to 40 mg every week or 80 mg every other week.

2.3 Recommended Dosage in Juvenile Idiopathic Arthritis or Pediatric Patients with Uveitis

The recommended subcutaneous dosage of Adalimumab-ryvk for pediatric patients 2 years of age and older with polyarticular juvenile idiopathic arthritis (JIA) or pediatric uveitis [see Indications and Usage (1.2, 1.9)],based on weight, is shown below. MTX, glucocorticoids, NSAIDs, and/or analgesics may be continued during treatment with Adalimumab-ryvk.

Pediatric Weight (2 Years of Age and Older) | Recommended Dosage
15 kg (33 lbs) to less than 30 kg (66 lbs) | 20 mg every other week
30 kg (66 lbs) and greater | 40 mg every other week

There is no dosage form for Adalimumab-ryvk that allows weight-based dosing for pediatric patients below 15 kg.

Adalimumab products have not been studied in patients with polyarticular JIA or pediatric uveitis less than 2 years of age or in patients with a weight below 10 kg.

2.4 Recommended Dosage in Crohn’s Disease

Subcutaneous Adult Dosage Regimen

The recommended subcutaneous dosage of Adalimumab-ryvk for adult patients with moderately to severely active Crohn’s disease (CD) is 160 mg initially on Day 1 (given in one day or split over two consecutive days), followed by 80 mg two weeks later (Day 15). Two weeks later (Day 29) begin a dosage of 40 mg every other week. Aminosalicylates and/or corticosteroids may be continued during treatment with Adalimumab-ryvk. Azathioprine, 6-mercaptopurine (6-MP) [see Warnings and Precautions (5.2)] or MTX may be continued during treatment with Adalimumab-ryvk if necessary.

Subcutaneous Pediatric Dosage Regimen

The recommended subcutaneous dosage of Adalimumab-ryvk for pediatric patients 6 years of age and older with moderately to severely active Crohn’s disease (CD), based on body weight, is shown below:

Pediatric Weight | Recommended Dosage
Pediatric Weight | Days 1 through 15 | Starting on Day 29
17 kg (37 lbs) to less than 40 kg (88 lbs) | Day 1: 80 mg; Day 15: 40 mg | 20 mg every other week
40 kg (88 lbs) and greater | Day 1: 160 mg (single dose or split over two consecutive days); Day 15: 80 mg | 40 mg every other week

2.5 Recommended Dosage in Ulcerative Colitis

Subcutaneous Adult Dosage Regimen

The recommended subcutaneous dosage of Adalimumab-ryvk for adult patients with moderately to severely active ulcerative colitis is 160 mg initially on Day 1 (given in one day or split over two consecutive days), followed by 80 mg two weeks later (Day 15). Two weeks later (Day 29) continue with a dosage of 40 mg every other week.

Discontinue Adalimumab-ryvk in adult patients without evidence of clinical remission by eight weeks (Day 57) of therapy. Aminosalicylates and/or corticosteroids may be continued during treatment with Adalimumab-ryvk. Azathioprine and 6-mercaptopurine (6-MP) [see Warnings and Precautions (5.2)] may be continued during treatment with Adalimumab-ryvk if necessary.

2.6 Recommended Dosage in Plaque Psoriasis or Adults with Uveitis

The recommended subcutaneous dosage of Adalimumab-ryvk for adult patients with plaque psoriasis (Ps) or uveitis (UV) [see Indications and Usage (1.7, 1.9)] is an initial dose of 80 mg, followed by 40 mg given every other week starting one week after the initial dose. The use of adalimumab products in moderate to severe chronic Ps beyond one year has not been evaluated in controlled clinical studies.

2.7 Recommended Dosage in Hidradenitis Suppurativa

Subcutaneous Adult Dosage Regimen

The recommended subcutaneous dosage of Adalimumab-ryvk for adult patients with moderate to severe hidradenitis suppurativa (HS) is an initial dose of 160 mg (given in one day or split over two consecutive days), followed by 80 mg two weeks later (Day 15). Begin 40 mg weekly or 80 mg every other week dosing two weeks later (Day 29).

Subcutaneous Pediatric Dosage Regimen

The recommended subcutaneous dosage of Adalimumab-ryvk for pediatric patients 12 years of age and older weighing at least 30 kg with moderate to severe hidradenitis suppurativa (HS), based on body weight, is shown below [see Use in Specific Populations (8.4) and Clinical Pharmacology (12.3)]:

Body Weight of Pediatric Patients; (12 years of age and older) | Recommended Dosage
30 kg (66 lbs) to less than 60 kg (132 lbs) | - Day 1: 80 mg - Day 8 and subsequent doses: 40 mg every other week
60 kg (132 lbs) and greater | - Day 1: 160 mg (given in one day or split over two consecutive days) - Day 15: 80 mg - Day 29 and subsequent doses: 40 mg every week or 80 mg every other week

2.8 General Considerations for Administration

Adalimumab-ryvk is intended for use under the guidance and supervision of a physician. A patient may self-inject Adalimumab-ryvk or a caregiver may inject Adalimumab-ryvk using either the Adalimumab-ryvk autoinjector or prefilled syringe if a physician determines that it is appropriate, and with medical follow-up, as necessary, after proper training in subcutaneous injection technique.

Adalimumab-ryvk can be taken out of the refrigerator for 15 to 30 minutes before injecting to allow the liquid to come to room temperature. Do not remove the cap or cover while allowing it to reach room temperature. Parenteral drug products should be inspected visually for particulate matter and discoloration prior to administration, whenever solution and container permit. If particulates and discolorations are noted, do not use the product. Adalimumab-ryvk does not contain preservatives; therefore, discard unused portions of drug remaining from the syringe.

Instruct patients using the Adalimumab-ryvk autoinjector or prefilled syringe to inject the full amount in the syringe, according to the directions provided in the Instructions for Use [see Instructions for Use].

Injections should occur at separate sites in the thigh or abdomen. Rotate injection sites and do not give injections into areas where the skin is tender, bruised, red or hard.

If a dose is missed, administer the dose as soon as possible. Thereafter, resume dosing at the regular scheduled time.

3 DOSAGE FORMS AND STRENGTHS

Adalimumab-ryvk is a clear and colorless solution available as:

- Autoinjector
  Injection: 80 mg/0.8 mL in a single-dose autoinjector.
  Injection: 40 mg/0.4 mL in a single-dose autoinjector.

- Prefilled Syringe
  Injection: 80 mg/0.8 mL in a single-dose prefilled glass syringe.

Injection: 40 mg/0.4 mL in a single-dose prefilled glass syringe.

Injection: 20 mg/0.2 mL in a single-dose prefilled glass syringe.

4 CONTRAINDICATIONS

None.

5 WARNINGS AND PRECAUTIONS

5.1 Serious Infections

Patients treated with adalimumab products, including Adalimumab-ryvk, are at increased risk for developing serious infections involving various organ systems and sites that may lead to hospitalization or death. Opportunistic infections due to bacterial, mycobacterial, invasive fungal, viral, parasitic, or other opportunistic pathogens including aspergillosis, blastomycosis, candidiasis, coccidioidomycosis, histoplasmosis, legionellosis, listeriosis, pneumocystosis and tuberculosis have been reported with TNF blockers. Patients have frequently presented with disseminated rather than localized disease.

The concomitant use of a TNF blocker and abatacept or anakinra was associated with a higher risk of serious infections in patients with rheumatoid arthritis (RA); therefore, the concomitant use of Adalimumab-ryvk and these biologic products is not recommended in the treatment of patients with RA [see Warnings and Precautions (5.7, 5.11) and Drug Interactions (7.2)].

Treatment with Adalimumab-ryvk should not be initiated in patients with an active infection, including localized infections. Patients 65 years of age and older, patients with co-morbid conditions and/or patients taking concomitant immunosuppressants (such as corticosteroids or methotrexate), may be at greater risk of infection. Consider the risks and benefits of treatment prior to initiating therapy in patients:

- with chronic or recurrent infection;
- who have been exposed to tuberculosis;
- with a history of an opportunistic infection;
- who have resided or traveled in areas of endemic tuberculosis or endemic mycoses, such as histoplasmosis, coccidioidomycosis, or blastomycosis; or
- with underlying conditions that may predispose them to infection.

Tuberculosis

Cases of reactivation of tuberculosis and new onset tuberculosis infections have been reported in patients receiving adalimumab products, including patients who have previously received treatment for latent or active tuberculosis. Reports included cases of pulmonary and extrapulmonary (i.e., disseminated) tuberculosis. Evaluate patients for tuberculosis risk factors and test for latent infection prior to initiating Adalimumab-ryvk and periodically during therapy.

Treatment of latent tuberculosis infection prior to therapy with TNF blocking agents has been shown to reduce the risk of tuberculosis reactivation during therapy. Prior to initiating Adalimumab-ryvk, assess if treatment for latent tuberculosis is needed; and consider an induration of ≥5 mm a positive tuberculin skin test result, even for patients previously vaccinated with Bacille Calmette-Guerin (BCG).

Consider anti-tuberculosis therapy prior to initiation of Adalimumab-ryvk in patients with a past history of latent or active tuberculosis in whom an adequate course of treatment cannot be confirmed, and for patients with a negative test for latent tuberculosis but having risk factors for tuberculosis infection. Despite prophylactic treatment for tuberculosis, cases of reactivated tuberculosis have occurred in patients treated with adalimumab products. Consultation with a physician with expertise in the treatment of tuberculosis is recommended to aid in the decision whether initiating anti-tuberculosis therapy is appropriate for an individual patient.

Strongly consider tuberculosis in the differential diagnosis in patients who develop a new infection during Adalimumab-ryvk treatment, especially in patients who have previously or recently traveled to countries with a high prevalence of tuberculosis, or who have had close contact with a person with active tuberculosis.

Monitoring

Closely monitor patients for the development of signs and symptoms of infection during and after treatment with Adalimumab-ryvk, including the development of tuberculosis in patients who tested negative for latent tuberculosis infection prior to initiating therapy. Tests for latent tuberculosis infection may also be falsely negative while on therapy with Adalimumab-ryvk.

Discontinue Adalimumab-ryvk if a patient develops a serious infection or sepsis. For a patient who develops a new infection during treatment with Adalimumab-ryvk, closely monitor them, perform a prompt and complete diagnostic workup appropriate for an immunocompromised patient, and initiate appropriate antimicrobial therapy.

Invasive Fungal Infections

If patients develop a serious systemic illness and they reside or travel in regions where mycoses are endemic, consider invasive fungal infection in the differential diagnosis. Antigen and antibody testing for histoplasmosis may be negative in some patients with active infection. Consider appropriate empiric antifungal therapy, taking into account both the risk for severe fungal infection and the risks of antifungal therapy, while a diagnostic workup is being performed. To aid in the management of such patients, consider consultation with a physician with expertise in the diagnosis and treatment of invasive fungal infections.

5.2 Malignancies

Consider the risks and benefits of TNF-blocker treatment including Adalimumab-ryvk prior to initiating therapy in patients with a known malignancy other than a successfully treated non-melanoma skin cancer (NMSC) or when considering continuing a TNF blocker in patients who develop a malignancy.

Malignancies in Adults

In the controlled portions of clinical trials of some TNF-blockers, including adalimumab products, more cases of malignancies have been observed among TNF-blocker-treated adult subjects compared to control-treated adult subjects. During the controlled portions of 39 global adalimumab clinical trials in adult patients with rheumatoid arthritis (RA), psoriatic arthritis (PsA), ankylosing spondylitis (AS), Crohn’s disease (CD), ulcerative colitis (UC), plaque psoriasis (Ps), hidradenitis suppurativa (HS) and uveitis (UV), malignancies, other than non-melanoma (basal cell and squamous cell) skin cancer, were observed at a rate (95% confidence interval) of 0.7 (0.48, 1.03) per 100 patient-years among 7973 adalimumab-treated subjects versus a rate of 0.7 (0.41, 1.17) per 100 patient-years among 4848 control-treated subjects (median duration of treatment of 4 months for adalimumab-treated subjects and 4 months for control-treated subjects). In 52 global controlled and uncontrolled clinical trials of adalimumab in adult patients with RA, PsA, AS, CD, UC, Ps, HS and UV, the most frequently observed malignancies, other than lymphoma and NMSC, were breast, colon, prostate, lung, and melanoma. The malignancies in adalimumab-treated subjects in the controlled and uncontrolled portions of the studies were similar in type and number to what would be expected in the general U.S. population according to the SEER database (adjusted for age, gender, and race).^1

In controlled trials of other TNF blockers in adult patients at higher risk for malignancies (i.e., subjects with COPD with a significant smoking history and cyclophosphamide-treated patients with Wegener’s granulomatosis), a greater portion of malignancies occurred in the TNF blocker group compared to the control group.

Non-Melanoma Skin Cancer

During the controlled portions of 39 global adalimumab clinical trials in adult patients with RA, PsA, AS, CD, UC, Ps, HS and UV, the rate (95% confidence interval) of NMSC was 0.8 (0.52, 1.09) per 100 patient-years among adalimumab-treated subjects and 0.2 (0.10, 0.59) per 100 patient-years among control-treated subjects. Examine all patients, and in particular patients with a medical history of prior prolonged immunosuppressant therapy or psoriasis patients with a history of PUVA treatment for the presence of NMSC prior to and during treatment with Adalimumab-ryvk.

Lymphoma and Leukemia

In the controlled portions of clinical trials of all the TNF-blockers in adults, more cases of lymphoma have been observed among TNF-blocker-treated subjects compared to control-treated subjects. In the controlled portions of 39 global adalimumab clinical trials in adult patients with RA, PsA, AS, CD, UC, Ps, HS and UV, 2 lymphomas occurred among 7973 adalimumab-treated subjects versus 1 among 4848 control-treated subjects. In 52 global controlled and uncontrolled clinical trials of adalimumab in adult patients with RA, PsA, AS, CD, UC, Ps, HS and UV with a median duration of approximately 0.7 years, including 24,605 subjects and over 40,215 patient-years of adalimumab, the observed rate of lymphomas was approximately 0.11 per 100 patient-years. This is approximately 3-fold higher than expected in the general U.S. population according to the SEER database (adjusted for age, gender, and race).^1 Rates of lymphoma in clinical trials of adalimumab cannot be compared to rates of lymphoma in clinical trials of other TNF blockers and may not predict the rates observed in a broader patient population. Patients with RA and other chronic inflammatory diseases, particularly those with highly active disease and/or chronic exposure to immunosuppressant therapies, may be at a higher risk (up to several fold) than the general population for the development of lymphoma, even in the absence of TNF blockers. Post-marketing cases of acute and chronic leukemia have been reported in association with TNF-blocker use in RA and other indications. Even in the absence of TNF-blocker therapy, patients with RA may be at a higher risk (approximately 2-fold) than the general population for the development of leukemia.

Malignancies in Pediatric Patients and Young Adults

Malignancies, some fatal, have been reported among children, adolescents, and young adults who received treatment with TNF-blockers (initiation of therapy ≤18 years of age), of which Adalimumab-ryvk is a member. Approximately half the cases were lymphomas, including Hodgkin's and non-Hodgkin's lymphoma. The other cases represented a variety of different malignancies and included rare malignancies usually associated with immunosuppression and malignancies that are not usually observed in children and adolescents. The malignancies occurred after a median of 30 months of therapy (range 1 to 84 months). Most of the patients were receiving concomitant immunosuppressants. These cases were reported post-marketing and are derived from a variety of sources including registries and spontaneous postmarketing reports.

Postmarketing cases of hepatosplenic T-cell lymphoma (HSTCL), a rare type of T-cell lymphoma, have been reported in patients treated with TNF blockers including adalimumab products. These cases have had a very aggressive disease course and have been fatal. The majority of reported TNF blocker cases have occurred in patients with Crohn's disease or ulcerative colitis and the majority were in adolescent and young adult males. Almost all of these patients had received treatment with the immunosuppressants azathioprine or
6-mercaptopurine (6-MP) concomitantly with a TNF blocker at or prior to diagnosis. It is uncertain whether the occurrence of HSTCL is related to use of a TNF blocker or a TNF blocker in combination with these other immunosuppressants. The potential risk with the combination of azathioprine or 6-mercaptopurine and Adalimumab-ryvk should be carefully considered.

5.3 Hypersensitivity Reactions

Anaphylaxis and angioneurotic edema have been reported following administration of adalimumab products. If an anaphylactic or other serious allergic reaction occurs, immediately discontinue administration of Adalimumab-ryvk and institute appropriate therapy. In clinical trials of adalimumab, hypersensitivity reactions (e.g., rash, anaphylactoid reaction, fixed drug reaction, non-specified drug reaction, urticaria) have been observed.

5.4 Hepatitis B Virus Reactivation

Use of TNF blockers, including Adalimumab-ryvk, may increase the risk of reactivation of hepatitis B virus (HBV) in patients who are chronic carriers of this virus. In some instances, HBV reactivation occurring in conjunction with TNF blocker therapy has been fatal. The majority of these reports have occurred in patients concomitantly receiving other medications that suppress the immune system, which may also contribute to HBV reactivation. Evaluate patients at risk for HBV infection for prior evidence of HBV infection before initiating TNF blocker therapy. Exercise caution in prescribing TNF blockers for patients identified as carriers of HBV. Adequate data are not available on the safety or efficacy of treating patients who are carriers of HBV with anti-viral therapy in conjunction with TNF blocker therapy to prevent HBV reactivation. For patients who are carriers of HBV and require treatment with TNF blockers, closely monitor such patients for clinical and laboratory signs of active HBV infection throughout therapy and for several months following termination of therapy. In patients who develop HBV reactivation, stop Adalimumab-ryvk and initiate effective anti-viral therapy with appropriate supportive treatment. The safety of resuming TNF blocker therapy after HBV reactivation is controlled is not known. Therefore, exercise caution when considering resumption of Adalimumab-ryvk therapy in this situation and monitor patients closely.

5.5 Neurologic Reactions

Use of TNF blocking agents, including adalimumab products, has been associated with rare cases of new onset or exacerbation of clinical symptoms and/or radiographic evidence of central nervous system demyelinating disease, including multiple sclerosis (MS) and optic neuritis, and peripheral demyelinating disease, including Guillain-Barré syndrome. Exercise caution in considering the use of Adalimumab-ryvk in patients with pre-existing or recent-onset central or peripheral nervous system demyelinating disorders; discontinuation of Adalimumab-ryvk should be considered if any of these disorders develop. There is a known association between intermediate uveitis and central demyelinating disorders.

5.6 Hematological Reactions

Rare reports of pancytopenia including aplastic anemia have been reported with TNF blocking agents. Adverse reactions of the hematologic system, including medically significant cytopenia (e.g., thrombocytopenia, leukopenia) have been infrequently reported with adalimumab products. The causal relationship of these reports to adalimumab products remains unclear. Advise all patients to seek immediate medical attention if they develop signs and symptoms suggestive of blood dyscrasias or infection (e.g., persistent fever, bruising, bleeding, pallor) while on Adalimumab-ryvk. Consider discontinuation of Adalimumab-ryvk therapy in patients with confirmed significant hematologic abnormalities.

5.7 Increased Risk of Infection when Used with Anakinra

Concurrent use of anakinra (an interleukin-1 antagonist) and another TNF-blocker, was associated with a greater proportion of serious infections and neutropenia and no added benefit compared with the TNF-blocker alone in patients with RA. Therefore, the combination of Adalimumab-ryvk and anakinra is not recommended [see Drug Interactions (7.2)].

5.8 Heart Failure

Cases of worsening congestive heart failure (CHF) and new onset CHF have been reported with TNF blockers. Cases of worsening CHF have also been observed with adalimumab products. Adalimumab products have not been formally studied in patients with CHF; however, in clinical trials of another TNF blocker, a higher rate of serious CHF-related adverse reactions was observed. Exercise caution when using Adalimumab-ryvk in patients who have heart failure and monitor them carefully.

5.9 Autoimmunity

Treatment with adalimumab products may result in the formation of autoantibodies and, rarely, in the development of a lupus-like syndrome or autoimmune hepatitis [see Adverse Reactions (6.1, 6.3)]. If a patient develops symptoms and findings suggestive of a lupus-like syndrome or autoimmune hepatitis following treatment with Adalimumab-ryvk, discontinue treatment and evaluate the patient.

5.10 Immunizations

In a placebo-controlled clinical trial of patients with RA, no difference was detected in anti-pneumococcal antibody response between adalimumab and placebo treatment groups when the pneumococcal polysaccharide vaccine and influenza vaccine were administered concurrently with adalimumab. Similar proportions of subjects developed protective levels of anti-influenza antibodies between adalimumab and placebo treatment groups; however, titers in aggregate to influenza antigens were moderately lower in patients receiving adalimumab. The clinical significance of this is unknown. Patients on Adalimumab-ryvk may receive concurrent vaccinations, except for live vaccines. No data are available on the secondary transmission of infection by live vaccines in patients receiving adalimumab products.

It is recommended that pediatric patients, if possible, be brought up to date with all immunizations in agreement with current immunization guidelines prior to initiating Adalimumab-ryvk therapy. Patients on Adalimumab-ryvk may receive concurrent vaccinations, except for live vaccines.

The safety of administering live or live-attenuated vaccines in infants exposed to adalimumab products in utero is unknown. Risks and benefits should be considered prior to vaccinating (live or live-attenuated) exposed infants [see Use in Specific Populations (8.1, 8.4)].

5.11 Increased Risk of Infection When Used with Abatacept

In controlled trials, the concurrent administration of TNF-blockers and abatacept was associated with a greater proportion of serious infections than the use of a TNF-blocker alone; the combination therapy, compared to the use of a TNF-blocker alone, has not demonstrated improved clinical benefit in the treatment of RA. Therefore, the combination of abatacept with TNF-blockers including Adalimumab-ryvk is not recommended [see Drug Interactions (7.2)].

6 ADVERSE REACTIONS

The following clinically significant adverse reactions are described elsewhere in the labeling:

- Serious Infections [see Warnings and Precautions (5.1)]
- Malignancies [see Warnings and Precautions (5.2)]
- Hypersensitivity Reactions [see Warnings and Precautions (5.3)]
- Hepatitis B Virus Reactivation [see Warnings and Precautions (5.4)]
- Neurologic Reactions [see Warnings and Precautions (5.5)]
- Hematological Reactions [see Warnings and Precautions (5.6)]
- Heart Failure [see Warnings and Precautions (5.8)]
- Autoimmunity [see Warnings and Precautions (5.9)]

6.1 Clinical Trials Experience

Because clinical trials are conducted under widely varying conditions, adverse reaction rates observed in the clinical trials of a drug cannot be directly compared to rates in the clinical trials of another drug and may not reflect the rates observed in practice.

The most common adverse reaction with adalimumab was injection site reactions. In placebo-controlled trials, 20% of subjects treated with adalimumab developed injection site reactions (erythema and/or itching, hemorrhage, pain or swelling), compared to 14% of subjects receiving placebo. Most injection site reactions were described as mild and generally did not necessitate drug discontinuation.

The proportion of subjects who discontinued treatment due to adverse reactions during the double-blind, placebo-controlled portion of studies in subjects with RA (i.e., Studies RA-I, RA-II, RA-III and RA-IV) was 7% for subjects taking adalimumab and 4% for placebo-treated subjects. The most common adverse reactions leading to discontinuation of adalimumab in these RA studies were clinical flare reaction (0.7%), rash (0.3%) and pneumonia (0.3%).

Infections

In the controlled portions of the 39 global adalimumab clinical trials in adult subjects with RA, PsA, AS, CD, UC, Ps, HS and UV, the rate of serious infections was 4.3 per 100 patient-years in 7973 adalimumab-treated subjects versus a rate of 2.9 per 100 patient-years in 4848 control-treated subjects. Serious infections observed included pneumonia, septic arthritis, prosthetic and post-surgical infections, erysipelas, cellulitis, diverticulitis, and pyelonephritis [see Warnings and Precautions (5.1)].

Tuberculosis and Opportunistic Infections

In 52 global controlled and uncontrolled clinical trials in RA, PsA, AS, CD, UC, Ps, HS and UV that included 24,605 adalimumab-treated subjects, the rate of reported active tuberculosis was 0.20 per 100 patient-years and the rate of positive PPD conversion was 0.09 per 100 patient-years. In a subgroup of 10,113 U.S. and Canadian adalimumab-treated subjects, the rate of reported active TB was 0.05 per 100 patient-years and the rate of positive PPD conversion was 0.07 per 100 patient-years. These trials included reports of miliary, lymphatic, peritoneal, and pulmonary TB. Most of the TB cases occurred within the first eight months after initiation of therapy and may reflect recrudescence of latent disease. In these global clinical trials, cases of serious opportunistic infections have been reported at an overall rate of 0.05 per 100 patient-years. Some cases of serious opportunistic infections and TB have been fatal [see Warnings and Precautions (5.1)].

Autoantibodies

In the rheumatoid arthritis controlled trials, 12% of subjects treated with adalimumab and 7% of placebo-treated subjects that had negative baseline ANA titers developed positive titers at week 24. Two subjects out of 3046 treated with adalimumab developed clinical signs suggestive of new-onset lupus-like syndrome. The subjects improved following discontinuation of therapy. No subjects developed lupus nephritis or central nervous system symptoms. The impact of long-term treatment with adalimumab products on the development of autoimmune diseases is unknown.

Liver Enzyme Elevations

There have been reports of severe hepatic reactions including acute liver failure in subjects receiving TNF-blockers. In controlled Phase 3 trials of adalimumab (40 mg SC every other week) in subjects with RA, PsA, and AS with control period duration ranging from 4 to 104 weeks, ALT elevations ≥3 x ULN occurred in 3.5% of adalimumab-treated subjects and 1.5% of control-treated subjects. Since many of these subjects in these trials were also taking medications that cause liver enzyme elevations (e.g., NSAIDS, MTX), the relationship between adalimumab and the liver enzyme elevations is not clear. In a controlled Phase 3 trial of adalimumab in subjects with polyarticular JIA who were 4 to 17 years, ALT elevations ≥3 x ULN occurred in 4.4% of adalimumab-treated subjects and 1.5% of control-treated subjects (ALT more common than AST); liver enzyme test elevations were more frequent among those treated with the combination of adalimumab and MTX than those treated with adalimumab alone. In general, these elevations did not lead to discontinuation of adalimumab treatment. No ALT elevations ≥3 x ULN occurred in the open-label study of adalimumab in subjects with polyarticular JIA who were 2 to <4 years.

In controlled Phase 3 trials of adalimumab (initial doses of 160 mg and 80 mg, or 80 mg and 40 mg on Days 1 and 15, respectively, followed by 40 mg every other week) in adult subjects with Crohn’s Disease with a control period duration ranging from 4 to 52 weeks, ALT elevations ≥3 x ULN occurred in 0.9% of adalimumab-treated subjects and 0.9% of control-treated subjects. In the Phase 3 trial of adalimumab in pediatric subjects with Crohn’s disease which evaluated efficacy and safety of two body weight based maintenance dose regimens following body weight based induction therapy up to 52 weeks of treatment, ALT elevations ≥3 x ULN occurred in 2.6% (5/192) of subjects, of whom 4 were receiving concomitant immunosuppressants at baseline; none of these subjects discontinued due to abnormalities in ALT tests. In controlled Phase 3 trials of adalimumab (initial doses of 160 mg and 80 mg on Days 1 and 15 respectively, followed by 40 mg every other week) in adult subjects with UC with control period duration ranging from 1 to 52 weeks, ALT elevations ≥3 x ULN occurred in 1.5% of adalimumab-treated subjects and 1.0% of control-treated subjects. In controlled Phase 3 trials of adalimumab (initial dose of 80 mg then 40 mg every other week) in subjects with Ps with control period duration ranging from 12 to 24 weeks, ALT elevations ≥3 x ULN occurred in 1.8% of adalimumab-treated subjects and 1.8% of control-treated subjects. In controlled trials of adalimumab (initial doses of 160 mg at Week 0 and 80 mg at Week 2, followed by 40 mg every week starting at Week 4), in subjects with HS with a control period duration ranging from 12 to 16 weeks, ALT elevations ≥ 3 x ULN occurred in 0.3% of adalimumab-treated subjects and 0.6% of control-treated subjects. In controlled trials of adalimumab (initial doses of 80 mg at Week 0 followed by 40 mg every other week starting at Week 1) in adult subjects with uveitis with an exposure of 165.4 PYs and 119.8 PYs in adalimumab-treated and control-treated subjects, respectively, ALT elevations ≥ 3 x ULN occurred in 2.4% of adalimumab-treated subjects and 2.4% of control-treated subjects.

Other Adverse Reactions

Rheumatoid Arthritis Clinical Studies

The data described below reflect exposure to adalimumab in 2468 subjects, including 2073 exposed for 6 months, 1497 exposed for greater than one year and 1380 in adequate and well-controlled studies (Studies RA-I, RA-II, RA-III, and RA-IV). Adalimumab was studied primarily in placebo-controlled trials and in long-term follow up studies for up to 36 months duration. The population had a mean age of 54 years, 77% were female, 91% were Caucasian and had moderately to severely active rheumatoid arthritis. Most subjects received 40 mg adalimumab every other week [see Clinical Studies (14.1)].

Table 1 summarizes reactions reported at a rate of at least 5% in subjects treated with adalimumab 40 mg every other week compared to placebo and with an incidence higher than placebo. In Study RA-III, the types and frequencies of adverse reactions in the second year open-label extension were similar to those observed in the one-year double-blind portion.

Table 1. Adverse Reactions Reported by ≥5% of Subjects Treated with Adalimumab During Placebo-Controlled Period of Pooled RA Studies (Studies RA-I, RA-II, RA-III, and RA-IV)
 | Adalimumab 40 mg subcutaneous Every Other Week | Placebo
 | (N=705) | (N=690)
Adverse Reaction (Preferred Term)
Respiratory
Upper respiratory infection | 17% | 13%
Sinusitis | 11% | 9%
Flu syndrome | 7% | 6%
Gastrointestinal
Nausea | 9% | 8%
Abdominal pain | 7% | 4%
Laboratory Tests*
Laboratory test abnormal | 8% | 7%
Hypercholesterolemia | 6% | 4%
Hyperlipidemia | 7% | 5%
Hematuria | 5% | 4%
Alkaline phosphatase increased | 5% | 3%
Other
Headache | 12% | 8%
Rash | 12% | 6%
Accidental injury | 10% | 8%
Injection site reaction** | 8% | 1%
Back pain | 6% | 4%
Urinary tract infection | 8% | 5%
Hypertension | 5% | 3%
*Laboratory test abnormalities were reported as adverse reactions in European trials
**Does not include injection site erythema, itching, hemorrhage, pain or swelling

Less Common Adverse Reactions in Rheumatoid Arthritis Clinical Studies

Other infrequent serious adverse reactions that do not appear in the Warnings and Precautions or Adverse Reaction sections that occurred at an incidence of less than 5% in adalimumab-treated subjects in RA studies (RA-I, RA-II, RA-III, and RA-IV) were:

Body As A Whole: Pain in extremity, pelvic pain, surgery, thorax pain

Cardiovascular System: Arrhythmia, atrial fibrillation, chest pain, coronary artery disorder, heart arrest, hypertensive encephalopathy, myocardial infarct, palpitation, pericardial effusion, pericarditis, syncope, tachycardia

Digestive System: Cholecystitis, cholelithiasis, esophagitis, gastroenteritis, gastrointestinal hemorrhage, hepatic necrosis, vomiting

Endocrine System: Parathyroid disorder

Hemic And Lymphatic System: Agranulocytosis, polycythemia

Metabolic And Nutritional Disorders: Dehydration, healing abnormal, ketosis, paraproteinemia, peripheral edema

Musculo-Skeletal System: Arthritis, bone disorder, bone fracture (not spontaneous), bone necrosis, joint disorder, muscle cramps, myasthenia, pyogenic arthritis, synovitis, tendon disorder

Neoplasia: Adenoma

Nervous System: Confusion, paresthesia, subdural hematoma, tremor

Respiratory System: Asthma, bronchospasm, dyspnea, lung function decreased, pleural effusion

Special Senses: Cataract

Thrombosis: Thrombosis leg

Urogenital System: Cystitis, kidney calculus, menstrual disorder

Juvenile Idiopathic Arthritis Clinical Studies

In general, the adverse reactions in the adalimumab-treated subjects in the polyarticular juvenile idiopathic arthritis (JIA) trials (Studies JIA-I and JIA-II) [see Clinical Studies (14.2)] were similar in frequency and type to those seen in adult subjects [see Warnings and Precautions (5), Adverse Reactions (6)]. Important findings and differences from adults are discussed in the following paragraphs.

In Study JIA-I, adalimumab was studied in 171 subjects who were 4 to 17 years of age, with polyarticular JIA. Severe adverse reactions reported in the study included neutropenia, streptococcal pharyngitis, increased aminotransferases, herpes zoster, myositis, metrorrhagia, and appendicitis. Serious infections were observed in 4% of subjects within approximately 2 years of initiation of treatment with adalimumab and included cases of herpes simplex, pneumonia, urinary tract infection, pharyngitis, and herpes zoster.

In Study JIA-I, 45% of subjects experienced an infection while receiving adalimumab with or without concomitant MTX in the first 16 weeks of treatment. The types of infections reported in adalimumab-treated subjects were generally similar to those commonly seen in polyarticular JIA subjects who are not treated with TNF blockers. Upon initiation of treatment, the most common adverse reactions occurring in this population treated with adalimumab were injection site pain and injection site reaction (19% and 16%, respectively). A less commonly reported adverse event in subjects receiving adalimumab was granuloma annulare which did not lead to discontinuation of adalimumab treatment.

In the first 48 weeks of treatment in Study JIA-I, non-serious hypersensitivity reactions were seen in approximately 6% of subjects and included primarily localized allergic hypersensitivity reactions and allergic rash.

In Study JIA-I, 10% of subjects treated with adalimumab who had negative baseline anti-dsDNA antibodies developed positive titers after 48 weeks of treatment. No subject developed clinical signs of autoimmunity during the clinical trial.

Approximately 15% of subjects treated with adalimumab developed mild-to-moderate elevations of creatine phosphokinase (CPK) in Study JIA-I. Elevations exceeding 5 times the upper limit of normal were observed in several subjects. CPK concentrations decreased or returned to normal in all subjects. Most subjects were able to continue adalimumab without interruption.

In Study JIA-II, adalimumab was studied in 32 subjects who were 2 to <4 years of age or 4 years of age and older weighing <15 kg with polyarticular JIA. The safety profile for this population was similar to the safety profile seen in subjects 4 to 17 years of age with polyarticular JIA.

In Study JIA-II, 78% of subjects experienced an infection while receiving adalimumab. These included nasopharyngitis, bronchitis, upper respiratory tract infection, otitis media, and were mostly mild to moderate in severity. Serious infections were observed in 9% of subjects receiving adalimumab in the study and included dental caries, rotavirus gastroenteritis, and varicella.

In Study JIA-II, non-serious allergic reactions were observed in 6% of subjects and included intermittent urticaria and rash, which were all mild in severity.

Psoriatic Arthritis and Ankylosing Spondylitis Clinical Studies

Adalimumab has been studied in 395 subjects with psoriatic arthritis (PsA) in two placebo-controlled trials and in an open label study and in 393 subjects with ankylosing spondylitis (AS) in two placebo-controlled studies [see Clinical Studies (14.3, 14.4)]. The safety profile for subjects with PsA and AS treated with adalimumab 40 mg every other week was similar to the safety profile seen in subjects with RA, adalimumab Studies RA-I through IV.

Crohn’s Disease Clinical Studies

Adults: The safety profile of adalimumab in 1478 adult subjects with Crohn’s disease from four placebo-controlled and two open-label extension studies [see Clinical Studies (14.5)] was similar to the safety profile seen in subjects with RA.

Pediatric Patients 6 Years to 17 Years: The safety profile of adalimumab in 192 pediatric subjects from one double-blind study (Study PCD-I) and one open-label extension study [see Clinical Studies (14.6)] was similar to the safety profile seen in adult subjects with Crohn’s disease.

During the 4-week open label induction phase of Study PCD-I, the most common adverse reactions occurring in the pediatric population treated with adalimumab were injection site pain and injection site reaction (6% and 5%, respectively).

A total of 67% of children experienced an infection while receiving adalimumab in Study PCD-I. These included upper respiratory tract infection and nasopharyngitis.

A total of 5% of children experienced a serious infection while receiving adalimumab in Study PCD-I. These included viral infection, device related sepsis (catheter), gastroenteritis, H1N1 influenza, and disseminated histoplasmosis.

In Study PCD-I, allergic reactions were observed in 5% of children which were all non-serious and were primarily localized reactions.

Ulcerative Colitis Clinical Studies

Adults: The safety profile of adalimumab in 1010 adult subjects with ulcerative colitis (UC) from two placebo-controlled studies and one open-label extension study [see Clinical Studies (14.7)] was similar to the safety profile seen in subjects with RA.

Plaque Psoriasis Clinical Studies

Adalimumab has been studied in 1696 subjects with plaque psoriasis (Ps) in placebo-controlled and open-label extension studies [see Clinical Studies (14.8)]. The safety profile for subjects with Ps treated with adalimumab was similar to the safety profile seen in subjects with RA with the following exceptions. In the placebo-controlled portions of the clinical trials in Ps subjects, adalimumab-treated subjects had a higher incidence of arthralgia when compared to controls (3% vs. 1%).

Hidradenitis Suppurativa Clinical Studies

Adalimumab has been studied in 727 subjects with hidradenitis suppurativa (HS) in three placebo-controlled studies and one open-label extension study [see Clinical Studies (14.9)]. The safety profile for subjects with HS treated with adalimumab weekly was consistent with the known safety profile of adalimumab.

Flare of HS, defined as ≥25% increase from baseline in abscesses and inflammatory nodule counts and with a minimum of 2 additional lesions, was documented in 22 (22%) of the 100 subjects who were withdrawn from adalimumab treatment following the primary efficacy timepoint in two studies.

Uveitis Clinical Studies

Adalimumab has been studied in 464 adult subjects with uveitis (UV) in placebo-controlled and open-label extension studies and in 90 pediatric subjects with uveitis (Study PUV-I) [see Clinical Studies (14.10, 14.11)]. The safety profile for subjects with UV treated with adalimumab was similar to the safety profile seen in subjects with RA.

6.2 Immunogenicity

The observed incidence of anti-drug antibodies is highly dependent on the sensitivity and specificity of the assay. Differences in assay methods preclude meaningful comparisons of the incidence of anti-drug antibodies in the studies described below with the incidence of anti-drug antibodies in other studies, including those of adalimumab or of other adalimumab products.

There are two assays that have been used to measure anti-adalimumab antibodies. With the ELISA, antibodies to adalimumab could be detected only when serum adalimumab concentrations were <2 mcg/mL. The ECL assay can detect anti-adalimumab antibody titers independent of adalimumab concentrations in the serum samples. The incidence of anti-adalimumab antibody (AAA) development in patients treated with adalimumab are presented in Table 2.

Table 2. Anti-Adalimumab Antibody Development Determined by ELISA and ECL Assay in Patients Treated with Adalimumab
Indications |  | Study Duration | Anti-Adalimumab Antibody; Incidence by ELISA (n/N) |  | Anti-Adalimumab Antibody; Incidence by ECL Assay (n/N)
Indications |  | Study Duration | In all patients who received adalimumab | In patients with serum adalimumab concentrations <2 mcg/mL
Rheumatoid Arthritisa |  | 6 to 12 months | 5% (58/1062) | NR | NA
Juvenile Idiopathic Arthritis (JIA) | 4 to 17 years of ageb | 48 weeks | 16% (27/171) | NR | NA
Juvenile Idiopathic Arthritis (JIA) | 2 to 4 years of age or ≥4 years of age and weighing <15 kg | 24 weeks | 7% (1/15)c | NR | NA
Psoriatic Arthritisd |  | 48 weekse | 13% (24/178) | NR | NA
Ankylosing Spondylitis |  | 24 weeks | 9% (16/185) | NR | NA
Adult Crohn’s Disease |  | 56 weeks | 3% (7/269) | 8% (7/86) | NA
Pediatric Crohn’s Disease |  | 52 weeks | 3% (6/182) | 10% (6/58) | NA
Adult Ulcerative Colitis |  | 52 weeks | 5% (19/360) | 21% (19/92) | NA
Plaque Psoriasisf |  | Up to 52 weeksg | 8% (77/920) | 21% (77/372) | NA
Hidradenitis Suppurativa |  | 36 weeks | 7% (30/461) | 28% (58/207)h | 61% (272/445)i
Non-infectious Uveitis |  | 52 weeks | 5% (12/249) | 21% (12/57) | 40% (99/249)j
n: number of patients with anti-adalimumab antibody; NR: not reported; NA: Not applicable (not performed)
aIn patients receiving concomitant methotrexate (MTX), the incidence of anti-adalimumab antibody was 1% compared to 12% with adalimumab monotherapy
bIn patients receiving concomitant MTX, the incidence of anti-adalimumab antibody was 6% compared to 26% with adalimumab monotherapy
cThis patient received concomitant MTX
dIn patients receiving concomitant MTX, the incidence of antibody development was 7% compared to 1% in RA
eSubjects enrolled after completing 2 previous studies of 24 weeks or 12 weeks of treatments.
fIn plaque psoriasis patients who were on adalimumab monotherapy and subsequently withdrawn from the treatment, the rate of antibodies to adalimumab after retreatment was similar to the rate observed prior to withdrawal
gOne 12-week Phase 2 study and one 52-week Phase 3 study
hAmong subjects in the 2 Phase 3 studies who stopped adalimumab treatment for up to 24 weeks and in whom adalimumab serum levels subsequently declined to <2 mcg/mL (approximately 22% of total subjects studied)
iNo correlation of antibody development to safety or efficacy outcomes was observed
jNo correlation of antibody development to safety or efficacy outcomes was observed

Rheumatoid Arthritis and Psoriatic Arthritis: Subjects in Studies RA-I, RA-II, and RA-III were tested at multiple time points for antibodies to adalimumab using the ELISA during the 6- to 12-month period. No apparent correlation of antibody development to adverse reactions was observed. With monotherapy, subjects receiving every other week dosing may develop antibodies more frequently than those receiving weekly dosing. In subjects receiving the recommended dosage of 40 mg every other week as monotherapy, the ACR 20 response was lower among antibody-positive subjects than among antibody-negative subjects. The long-term immunogenicity of adalimumab products is unknown.

6.3 Postmarketing Experience

The following adverse reactions have been identified during post-approval use of adalimumab products. Because these reactions are reported voluntarily from a population of uncertain size, it is not always possible to reliably estimate their frequency or establish a causal relationship to adalimumab products exposure.

Gastrointestinal disorders: Diverticulitis, large bowel perforations including perforations associated with diverticulitis and appendiceal perforations associated with appendicitis, pancreatitis

General disorders and administration site conditions: Pyrexia

Hepato-biliary disorders: Liver failure, hepatitis, autoimmune hepatitis

Immune system disorders: Sarcoidosis

Neoplasms benign, malignant and unspecified (including cysts and polyps): Merkel Cell Carcinoma (neuroendocrine carcinoma of the skin)

Nervous system disorders: Demyelinating disorders (e.g., optic neuritis, Guillain-Barré syndrome), cerebrovascular accident

Respiratory disorders: Interstitial lung disease, including pulmonary fibrosis, pulmonary embolism

Skin reactions: Stevens Johnson Syndrome, cutaneous vasculitis, erythema multiforme, new or worsening psoriasis (all sub-types including pustular and palmoplantar), alopecia, lichenoid skin reaction

Vascular disorders: Systemic vasculitis, deep vein thrombosis

7 DRUG INTERACTIONS

7.1 Methotrexate

Adalimumab has been studied in rheumatoid arthritis (RA) patients taking concomitant methotrexate (MTX). Although MTX reduced the apparent clearance of adalimumab, the data do not suggest the need for dose adjustment of either Adalimumab-ryvk or MTX [see Clinical Pharmacology (12.3)].

7.2 Biological Products

In clinical studies in patients with RA, an increased risk of serious infections has been observed with the combination of TNF blockers with anakinra or abatacept, with no added benefit; therefore, use of Adalimumab-ryvk with abatacept or anakinra is not recommended in patients with RA [see Warnings and Precautions (5.7, 5.11)]. A higher rate of serious infections has also been observed in patients with RA treated with rituximab who received subsequent treatment with a TNF blocker. There is insufficient information regarding the concomitant use of Adalimumab-ryvk and other biologic products for the treatment of RA, PsA, AS, CD, UC, Ps, HS, and UV. Concomitant administration of Adalimumab-ryvk with other biologic DMARDS (e.g., anakinra and abatacept) or other TNF blockers is not recommended based upon the possible increased risk for infections and other potential pharmacological interactions.

7.3 Live Vaccines

Avoid the use of live vaccines with Adalimumab-ryvk [see Warnings and Precautions (5.10)].

7.4 Cytochrome P450 Substrates

The formation of CYP450 enzymes may be suppressed by increased concentrations of cytokines (e.g., TNFα, IL-6) during chronic inflammation. It is possible for products that antagonize cytokine activity, such as adalimumab products, to influence the formation of CYP450 enzymes. Upon initiation or discontinuation of Adalimumab-ryvk in patients being treated with CYP450 substrates with a narrow therapeutic index, monitoring of the effect (e.g., warfarin) or drug concentration (e.g., cyclosporine or theophylline) is recommended and the individual dose of the drug product may be adjusted as needed.

8 USE IN SPECIFIC POPULATIONS

8.1 Pregnancy

Risk Summary

Available studies with use of adalimumab during pregnancy do not reliably establish an association between adalimumab and major birth defects. Clinical data are available from the Organization of Teratology Information Specialists (OTIS)/MotherToBaby Pregnancy Registry in pregnant women with rheumatoid arthritis (RA) or Crohn’s disease (CD) treated with adalimumab. Registry results showed a rate of 10% for major birth defects with first trimester use of adalimumab in pregnant women with RA or CD and a rate of 7.5% for major birth defects in the disease-matched comparison cohort. The lack of pattern of major birth defects is reassuring and differences between exposure groups may have impacted the occurrence of birth defects (see Data).

Adalimumab is actively transferred across the placenta during the third trimester of pregnancy and may affect immune response in the in-utero exposed infant (see Clinical Considerations). In an embryo-fetal perinatal development study conducted in cynomolgus monkeys, no fetal harm or malformations were observed with intravenous administration of adalimumab during organogenesis and later in gestation, at doses that produced exposures up to approximately 373 times the maximum recommended human dose (MRHD) of 40 mg subcutaneous without methotrexate (see Data).

The estimated background risk of major birth defects and miscarriage for the indicated populations is unknown. All pregnancies have a background risk of birth defect, loss, or other adverse outcomes. In the U.S. general population, the estimated background risk of major birth defects and miscarriage in clinically recognized pregnancies is 2% to 4% and 15% to 20%, respectively.

Clinical Considerations

Disease-associated maternal and embryo/fetal risk

Published data suggest that the risk of adverse pregnancy outcomes in women with RA or inflammatory bowel disease (IBD) is associated with increased disease activity. Adverse pregnancy outcomes include preterm delivery (before 37 weeks of gestation), low birth weight (less than 2500 g) infants, and small for gestational age at birth.

Fetal/Neonatal Adverse Reactions

Monoclonal antibodies are increasingly transported across the placenta as pregnancy progresses, with the largest amount transferred during the third trimester [see Data]. Risks and benefits should be considered prior to administering live or live-attenuated vaccines to infants exposed to adalimumab products in utero [see Use in Specific Populations (8.4)].

Data

Human Data

A prospective cohort pregnancy exposure registry conducted by OTIS/MotherToBaby in the U.S. and Canada between 2004 and 2016 compared the risk of major birth defects in live-born infants of 221 women (69 RA, 152 CD) treated with adalimumab during the first trimester and 106 women (74 RA, 32 CD) not treated with adalimumab.

The proportion of major birth defects among live-born infants in the adalimumab-treated and untreated cohorts was 10% (8.7% RA, 10.5% CD) and 7.5% (6.8% RA, 9.4% CD), respectively. The lack of pattern of major birth defects is reassuring and differences between exposure groups may have impacted the occurrence of birth defects. This study cannot reliably establish whether there is an association between adalimumab and major birth defects because of methodological limitations of the registry, including small sample size, the voluntary nature of the study, and the non-randomized design.

In an independent clinical study conducted in ten pregnant women with IBD treated with adalimumab, adalimumab concentrations were measured in maternal serum as well as in cord blood (n=10) and infant serum (n=8) on the day of birth. The last dose of adalimumab was given between 1 and 56 days prior to delivery. Adalimumab concentrations were 0.16 to 19.7 mcg/mL in cord blood, 4.28 to 17.7 mcg/mL in infant serum, and 0 to 16.1 mcg/mL in maternal serum. In all but one case, the cord blood concentration of adalimumab was higher than the maternal serum concentration, suggesting adalimumab actively crosses the placenta. In addition, one infant had serum concentrations at each of the following: 6 weeks (1.94 mcg/mL), 7 weeks (1.31 mcg/mL), 8 weeks (0.93 mcg/mL), and 11 weeks (0.53 mcg/mL), suggesting adalimumab can be detected in the serum of infants exposed in utero for at least 3 months from birth.

Animal Data

In an embryo-fetal perinatal development study, pregnant cynomolgus monkeys received adalimumab from gestation days 20 to 97 at doses that produced exposures up to 373 times that achieved with the MRHD without methotrexate (on an AUC basis with maternal IV doses up to 100 mg/kg/week). Adalimumab did not elicit harm to the fetuses or malformations.

8.2 Lactation

Risk Summary

Limited data from case reports in the published literature describe the presence of adalimumab in human milk at infant doses of 0.1% to 1% of the maternal serum concentration. Published data suggest that the systemic exposure to a breastfed infant is expected to be low because adalimumab is a large molecule and is degraded in the gastrointestinal tract. However, the effects of local exposure in the gastrointestinal tract are unknown. There are no reports of adverse effects of adalimumab products on the breastfed infant and no effects on milk production. The developmental and health benefits of breastfeeding should be considered along with the mother’s clinical need for Adalimumab-ryvk and any potential adverse effects on the breastfed child from Adalimumab-ryvk or from the underlying maternal condition.

8.4 Pediatric Use

The safety and effectiveness of adalimumab products have not been established in pediatric patients with psoriatic arthritis, ankylosing spondylitis, or plaque psoriasis.

The safety and effectiveness of Adalimumab-ryvk have been established for:

- reducing signs and symptoms of moderately to severely active polyarticular JIA in pediatric patients 2 years of age and older.
- the treatment of moderately to severely active Crohn’s disease in pediatric patients 6 years of age and older.
- the treatment of moderate to severe hidradenitis suppurativa in patients 12 years of age and older.
- the treatment of non-infectious intermediate, posterior, and panuveitis in pediatric patients 2 years of age and older.

A Pediatric assessment for Adalimumab-ryvk demonstrate that Adalimumab-ryvk is safe and effective for pediatric patients in an indication for which Humira® (adalimumab) is approved. However, Adalimumab-ryvk is not approved for such indication due to marketing exclusivity for Humira (adalimumab).

Due to their inhibition of TNFα, adalimumab products administered during pregnancy could affect immune response in the in utero-exposed newborn and infant. Data from eight infants exposed to adalimumab in utero suggest adalimumab crosses the placenta [see Use in Specific Populations (8.1)]. The clinical significance of elevated adalimumab concentrations in infants is unknown. The safety of administering live or live-attenuated vaccines in exposed infants is unknown. Risks and benefits should be considered prior to vaccinating (live or live-attenuated) exposed infants.

Post-marketing cases of lymphoma, including hepatosplenic T-cell lymphoma and other malignancies, some fatal, have been reported among children, adolescents, and young adults who received treatment with TNF-blockers including adalimumab products [see Warnings and Precautions (5.2)].

Juvenile Idiopathic Arthritis

The safety and effectiveness of Adalimumab-ryvk for the treatment of moderately to severely active polyarticular JIA have been established in pediatric patients 2 years of age and older. Use for this indication is supported by evidence from an adequate and well-controlled study (Study JIA) of adalimumab in patients 4 to 17 years of age [see Clinical Studies (14.2)] and a safety study (Study JIA-II) in patients of adalimumab 2 to <4 years of age where the safety profile was similar to patients 4 to 17 years of age[see Adverse Reactions (6.1)]. Adalimumab products have not been studied in patients with polyarticular JIA less than 2 years of age or in patients with a weight below 10 kg.

The safety of adalimumab in pediatric patients in the polyarticular JIA trials was generally similar to that observed in adults with certain exceptions [see Adverse Reactions (6.1)].

The safety and effectiveness of Adalimumab-ryvk have not been established in pediatric patients with JIA less than 2 years of age.

Pediatric Crohn’s Disease

The safety and effectiveness of Adalimumab-ryvk for the treatment of moderately to severely active Crohn’s disease have been established in pediatric patients 6 years of age and older. Use of Adalimumab-ryvk for this indication is supported by evidence from adequate and well-controlled studies in adults with additional data from a randomized, double-blind, 52‑week clinical study of two dose concentrations of adalimumab in 192 pediatric patients (6 years to 17 years of age) [see Adverse Reactions (6.1), Clinical Pharmacology (12.2, 12.3), Clinical Studies (14.6)]. The adverse reaction profile in patients 6 years to 17 years of age was similar to adults.

The safety and effectiveness of Adalimumab-ryvk have not been established in pediatric patients with Crohn’s disease less than 6 years of age.

Pediatric Uveitis

The safety and effectiveness of Adalimumab-ryvk for the treatment of non-infectious, intermediate, posterior, and panuveitis have been established in pediatric patients 2 years of age and older. The use of adalimumab for this indication is supported by evidence from adequate and well-controlled studies of adalimumab in adults and a 2:1 randomized, controlled clinical study in 90 pediatric patients [see Clinical Studies (14.11)]. The safety and effectiveness of adalimumab products have not been established in pediatric patients with uveitis less than 2 years of age.

Hidradenitis Suppurativa

Use of Adalimumab-ryvk in pediatric patients 12 years of age and older for the treatment of moderate to severe HS is supported by evidence from adequate and well-controlled studies of adalimumab in adult HS patients. Additional population pharmacokinetic modeling and simulation predicted that weight-based dosing of adalimumab in pediatric patients 12 years of age and older can provide generally similar exposure to adult HS patients. The course of HS is sufficiently similar in adult and adolescent patients to allow extrapolation of data from adult to adolescent patients. The recommended dosage in pediatric patients 12 years of age or older is based on body weight [see Dosage and Administration (2.7), Clinical Pharmacology (12.3), and Clinical Studies (14.9)].

The safety and effectiveness of Adalimumab-ryvk have not been established in patients less than 12 years of age with HS.

8.5 Geriatric Use

In clinical studies of RA (Studies RA-I, RA-II, RA-III, and RA-IV), a total of 519 subjects 65 years of age and older, including 107 subjects 75 years of age and older, received adalimumab. No overall difference in effectiveness was observed between these subjects and younger adult subjects.

The frequency of serious infection and malignancy among adalimumab treated subjects 65 years of age and older was higher than for those less than 65 years of age. Consider the benefits and risks of Adalimumab-ryvk in patients 65 years of age and older. In patients treated with Adalimumab-ryvk, closely monitor for the development of infection or malignancy [see Warnings and Precautions (5.1, 5.2)].

10 OVERDOSAGE

Doses up to 10 mg/kg have been administered to patients in clinical trials without evidence of dose-limiting toxicities. In case of overdosage, it is recommended that the patient be monitored for any signs or symptoms of adverse reactions or effects and appropriate symptomatic treatment instituted immediately.

Consider contacting the Poison Help line (1-800-222-1222) or medical toxicologist for additional overdose management recommendations.

11 DESCRIPTION

Adalimumab-ryvk is a tumor necrosis factor blocker. Adalimumab-ryvk is a recombinant human IgG1 monoclonal antibody with human derived heavy and light chain variable regions and human IgG1:k constant regions. Adalimumab-ryvk is produced by recombinant DNA technology in a mammalian cell (Chinese Hamster Ovary (CHO)) expression system and is purified by a process that includes specific viral inactivation and removal steps. It consists of 1330 amino acids and has a molecular weight of approximately 148 kilodaltons.

Adalimumab-ryvk injection is supplied as a sterile, preservative-free solution for subcutaneous administration. The drug product is supplied as either a single-dose, prefilled Adalimumab-ryvk autoinjector or as a single-dose, 1 mL prefilled glass syringe. Enclosed within the autoinjector is a single-dose, 1 mL prefilled glass syringe. The solution of Adalimumab-ryvk is clear and colorless, with a pH of 5.0-5.6.

Each 80 mg/0.8 mL prefilled syringe or prefilled autoinjector delivers 0.8 mL (80 mg) of drug product. Each 0.8 mL of Adalimumab-ryvk contains adalimumab-ryvk (80 mg), polysorbate 80 (0.80 mg), sodium chloride (0.47 mg), sucrose (69.83 mg), and Water for Injection, USP. Sodium hydroxide and hydrochloric acid are added as necessary to adjust pH.

Each 40 mg/0.4 mL prefilled syringe or prefilled autoinjector delivers 0.4 mL (40 mg) of drug product. Each 0.4 mL of Adalimumab-ryvk contains adalimumab-ryvk (40 mg), polysorbate 80 (0.40 mg), sodium chloride (0.23 mg), sucrose (34.9 mg), and Water for Injection, USP. Sodium hydroxide and hydrochloric acid are added as necessary to adjust pH.

Each 20 mg/0.2 mL prefilled syringe delivers 0.2 mL (20 mg) of drug product. Each 0.2 mL of Adalimumab-ryvk contains adalimumab-ryvk (20 mg), polysorbate 80 (0.20 mg), sodium chloride (0.12 mg), sucrose (17.46 mg), and Water for Injection, USP. Sodium hydroxide and hydrochloric acid are added as necessary to adjust pH.

12 CLINICAL PHARMACOLOGY

12.1 Mechanism of Action

Adalimumab products bind specifically to TNF-alpha and block its interaction with the p55 and p75 cell surface TNF receptors. Adalimumab products also lyse surface TNF expressing cells in vitro in the presence of complement. Adalimumab products do not bind or inactivate lymphotoxin (TNF-beta). TNF is a naturally occurring cytokine that is involved in normal inflammatory and immune responses. Elevated concentrations of TNF are found in the synovial fluid of patients with RA, JIA, PsA, and AS and play an important role in both the pathologic inflammation and the joint destruction that are hallmarks of these diseases. Increased concentrations of TNF are also found in psoriasis plaques. In Ps, treatment with Adalimumab-ryvk may reduce the epidermal thickness and infiltration of inflammatory cells. The relationship between these pharmacodynamic activities and the mechanism(s) by which adalimumab products exert their clinical effects is unknown.

Adalimumab products also modulate biological responses that are induced or regulated by TNF, including changes in the concentrations of adhesion molecules responsible for leukocyte migration (ELAM-1, VCAM-1, and ICAM-1 with an IC50 of 1-2 X 10^-10M).

12.2 Pharmacodynamics

After treatment with adalimumab, a decrease in concentrations of acute phase reactants of inflammation (C-reactive protein [CRP] and erythrocyte sedimentation rate [ESR]) and serum cytokines (IL-6) was observed compared to baseline in patients with rheumatoid arthritis. A decrease in CRP concentrations was also observed in patients with Crohn’s disease, ulcerative colitis and hidradenitis suppurativa. Serum concentrations of matrix metalloproteinases (MMP-1 and MMP-3) that produce tissue remodeling responsible for cartilage destruction were also decreased after adalimumab administration.

12.3 Pharmacokinetics

The pharmacokinetics of adalimumab were linear over the dose range of 0.5 to 10 mg/kg following administration of a single intravenous dose (adalimumab products are not approved for intravenous use). Following 20, 40, and 80 mg every other week and every week subcutaneous administration, adalimumab mean serum trough concentrations at steady state increased approximately proportionally with dose in RA patients. The mean terminal half-life was approximately 2 weeks, ranging from 10 to 20 days across studies. Healthy subjects and patients with RA displayed similar adalimumab pharmacokinetics.

Adalimumab exposure in patients treated with 80 mg every other week is estimated to be comparable with that in patients treated with 40 mg every week.

Absorption

The average absolute bioavailability of adalimumab following a single 40 mg subcutaneous dose was 64%. The mean time to reach the maximum concentration was 5.5 days (131±56 hours) and the maximum serum concentration was 4.7±1.6 mcg/mL in healthy subjects following a single 40 mg subcutaneous administration of adalimumab.

Distribution

The distribution volume (Vss) ranged from 4.7 to 6.0 L following intravenous administration of doses ranging from 0.25 to 10 mg/kg in RA patients.

Elimination

The single dose pharmacokinetics of adalimumab in RA patients were determined in several studies with intravenous doses ranging from 0.25 to 10 mg/kg. The systemic clearance of adalimumab is approximately 12 mL/hr. In long-term studies with dosing more than two years, there was no evidence of changes in clearance over time in RA patients.

Patient Population

Rheumatoid Arthritis and Ankylosing Spondylitis: In patients receiving 40 mg adalimumab every other week, adalimumab mean steady-state trough concentrations were approximately 5 mcg/mL and 8 to 9 mcg/mL, without and with MTX concomitant treatment, respectively. Adalimumab concentrations in the synovial fluid from five rheumatoid arthritis patients ranged from 31 to 96% of those in serum. The pharmacokinetics of adalimumab in patients with AS were similar to those in patients with RA.

Psoriatic Arthritis: In patients receiving 40 mg every other week, adalimumab mean steady-state trough concentrations were 6 to 10 mcg/mL and 8.5 to 12 mcg/mL, without and with MTX concomitant treatment, respectively.

Plaque Psoriasis: Adalimumab mean steady-state trough concentration was approximately 5 to 6 mcg/mL during adalimumab 40 mg every other week treatment.

Adult Uveitis: Adalimumab mean steady concentration was approximately 8 to 10 mcg/mL during adalimumab 40 mg every other week treatment.

Adult Hidradenitis Suppurativa: Adalimumab trough concentrations were approximately 7 to 8 mcg/mL at Week 2 and Week 4, respectively, after receiving 160 mg on Week 0 followed by 80 mg on Week 2. Mean steady-state trough concentrations at Week 12 through Week 36 were approximately 7 to 11 mcg/mL during adalimumab 40 mg every week treatment.

Adult Crohn’s Disease: Adalimumab mean trough concentrations were approximately 12 mcg/mL at Week 2 and Week 4 after receiving 160 mg on Week 0 followed by 80 mg on Week 2. Mean steady-state trough concentrations were 7 mcg/mL at Week 24 and Week 56 during adalimumab 40 mg every other week treatment.

Adult Ulcerative Colitis: Adalimumab mean trough concentrations were approximately 12 mcg/mL at Week 2 and Week 4 after receiving 160 mg on Week 0 followed by 80 mg on Week 2. Mean steady-state trough concentrations were approximately 8 mcg/mL and 15 mcg/mL at Week 52 after receiving a dose of adalimumab 40 mg every other week and 40 mg every week, respectively.

Anti-Drug Antibody Effects on Pharmacokinetics

Rheumatoid Arthritis: A trend toward higher apparent clearance of adalimumab in the presence of anti-adalimumab antibodies was identified.

Hidradenitis Suppurativa: In subjects with moderate to severe HS, antibodies to adalimumab were associated with reduced serum adalimumab concentrations. In general, the extent of reduction in serum adalimumab concentrations is greater with increasing titers of antibodies to adalimumab.

Specific Populations

Geriatric Patients: A lower clearance with increasing age was observed in patients with RA aged 40 to >75 years.

Pediatric Patients:

Juvenile Idiopathic Arthritis:

- 4 years to 17 years of age: The adalimumab mean steady-state trough concentrations were 6.8 mcg/mL and 10.9 mcg/mL in patients weighing <30 kg receiving 20 mg adalimumab subcutaneously every other week as monotherapy or with concomitant MTX, respectively. The adalimumab mean steady-state trough concentrations were 6.6 mcg/mL and 8.1 mcg/mL in patients weighing ≥30 kg receiving 40 mg adalimumab subcutaneously every other week as monotherapy or with MTX concomitant treatment, respectively.
- 2 years to <4 years of age or 4 years of age and older weighing <15 kg: The adalimumab mean steady-state trough adalimumab concentrations were 6.0 mcg/mL and 7.9 mcg/mL in patients receiving adalimumab subcutaneously every other week as monotherapy or with MTX concomitant treatment, respectively.

Pediatric Hidradenitis Suppurativa: Adalimumab concentrations in adolescent patients with HS receiving the recommended dosage regimens are predicted to be similar to those observed in adult subjects with HS based on population pharmacokinetic modeling and simulation.

Pediatric Crohn’s Disease: Adalimumab mean ± SD concentrations were 15.7±6.5 mcg/mL at Week 4 following 160 mg at Week 0 and 80 mg at Week 2, and 10.5±6.0 mcg/mL at Week 52 following 40 mg every other week dosing in patients weighing ≥40 kg. Adalimumab mean ± SD concentrations were 10.6±6.1 mcg/mL at Week 4 following dosing 80 mg at Week 0 and 40 mg at Week 2, and 6.9±3.6 mcg/mL at Week 52 following 20 mg every other week dosing in patients weighing <40 kg.

Male and Female Patients: No gender-related pharmacokinetic differences were observed after correction for a patient’s body weight. Healthy subjects and patients with rheumatoid arthritis displayed similar adalimumab pharmacokinetics.

Patients with Renal or Hepatic Impairment: No pharmacokinetic data are available in patients with hepatic or renal impairment.

Rheumatoid factor or CRP concentrations: Minor increases in apparent clearance were predicted in RA patients receiving doses lower than the recommended dose and in RA patients with high rheumatoid factor or CRP concentrations. These increases are not likely to be clinically important.

Drug Interaction Studies:

Methotrexate: MTX reduced adalimumab apparent clearance after single and multiple dosing by 29% and 44% respectively, in patients with RA [see Drug Interactions (7.1)].

13 NONCLINICAL TOXICOLOGY

13.1 Carcinogenesis, Mutagenesis, Impairment of Fertility

Long-term animal studies of adalimumab products have not been conducted to evaluate the carcinogenic potential or its effect on fertility.

14 CLINICAL STUDIES

14.1 Clinical Studies in Rheumatoid Arthritis

The efficacy and safety of adalimumab were assessed in five randomized, double-blind studies in subjects ≥18 years of age with active rheumatoid arthritis (RA) diagnosed according to American College of Rheumatology (ACR) criteria. Subjects had at least 6 swollen and 9 tender joints. Adalimumab was administered subcutaneously in combination with methotrexate (MTX) (12.5 to 25 mg, Studies RA-I, RA-III and RA-V) or as monotherapy (Studies RA-II and RA-V) or with other disease-modifying anti-rheumatic drugs (DMARDs) (Study RA-IV).

Study RA-I evaluated 271 subjects who had failed therapy with at least one but no more than four DMARDs and had inadequate response to MTX. Doses of 20, 40 or 80 mg of adalimumab or placebo were given every other week for 24 weeks.

Study RA-II evaluated 544 subjects who had failed therapy with at least one DMARD. Doses of placebo, 20 or 40 mg of adalimumab were given as monotherapy every other week or weekly for 26 weeks.

Study RA-III evaluated 619 subjects who had an inadequate response to MTX. Subjects received placebo, 40 mg of adalimumab every other week with placebo injections on alternate weeks, or 20 mg of adalimumab weekly for up to 52 weeks. Study RA-III had an additional primary endpoint at 52 weeks of inhibition of disease progression (as detected by X-ray results). Upon completion of the first 52 weeks, 457 subjects enrolled in an open-label extension phase in which 40 mg of adalimumab was administered every other week for up to 5 years.

Study RA-IV assessed safety in 636 subjects who were either DMARD-naive or were permitted to remain on their pre-existing rheumatologic therapy provided that therapy was stable for a minimum of 28 days. Subjects were randomized to 40 mg of adalimumab or placebo every other week for 24 weeks.

Study RA-V evaluated 799 subjects with moderately to severely active RA of less than 3 years duration who were ≥18 years old and MTX naïve. Subjects were randomized to receive either MTX (optimized to 20 mg/week by week 8), adalimumab 40 mg every other week or adalimumab/MTX combination therapy for 104 weeks. Subjects were evaluated for signs and symptoms, and for radiographic progression of joint damage. The median disease duration among subjects enrolled in the study was 5 months. The median MTX dose achieved was 20 mg.

Clinical Response

The percent of adalimumab treated subjects achieving ACR 20, 50 and 70 responses in Studies RA-II and III are shown in Table 3.

Table 3. ACR Responses in Studies RA-II and RA-III (Percent of Subjects)
 | Study RA-II; Monotherapy; (26 weeks) |  |  | Study RA-III; Methotrexate Combination; (24 and 52 weeks)
Response | Placebo | Adalimumab 40 mg every other week | Adalimumab 40 mg weekly | Placebo/MTX | Adalimumab/MTX; 40 mg every other week
 | N=110 | N=113 | N=103 | N=200 | N=207
ACR20
Month 6 | 19% | 46%* | 53%* | 30% | 63%*
Month 12 | NA | NA | NA | 24% | 59%*
ACR50
Month 6 | 8% | 22%* | 35%* | 10% | 39%*
Month 12 | NA | NA | NA | 10% | 42%*
ACR70
Month 6 | 2% | 12%* | 18%* | 3% | 21%*
Month 12 | NA | NA | NA | 5% | 23%*
*p<0.01, adalimumab vs. placebo

The results of Study RA-I were similar to Study RA-III; subjects receiving adalimumab 40 mg every other week in Study RA-I also achieved ACR 20, 50 and 70 response rates of 65%, 52% and 24%, respectively, compared to placebo responses of 13%, 7% and 3% respectively, at 6 months (p<0.01).

The results of the components of the ACR response criteria for Studies RA-II and RA-III are shown in Table 4. ACR response rates and improvement in all components of ACR response were maintained to week 104. Over the 2 years in Study RA-III, 20% of adalimumab subjects receiving 40 mg every other week achieved a major clinical response, defined as maintenance of an ACR 70 response over a 6-month period. ACR responses were maintained in similar proportions of subjects for up to 5 years with continuous adalimumab treatment in the open-label portion of Study RA-III.

Table 4. Components of ACR Response in Studies RA-II and RA-III
 | Study RA-II |  |  |  | Study RA-III
Parameter (median) | Placebo; N=110 |  | Adalimumaba; N=113 |  | Placebo/MTX N=200 |  | Adalimumaba/MTX N=207
 | Baseline | Wk 26 | Baseline | Wk 26 | Baseline | Wk 24 | Baseline | Wk 24
Number of tender joints (0-68) | 35 | 26 | 31 | 16* | 26 | 15 | 24 | 8*
Number of swollen joints (0-66) | 19 | 16 | 18 | 10* | 17 | 11 | 18 | 5*
Physician global; assessmentb | 7.0 | 6.1 | 6.6 | 3.7* | 6.3 | 3.5 | 6.5 | 2.0*
Patient global assessmentb | 7.5 | 6.3 | 7.5 | 4.5* | 5.4 | 3.9 | 5.2 | 2.0*
Painb | 7.3 | 6.1 | 7.3 | 4.1* | 6.0 | 3.8 | 5.8 | 2.1*
Disability index (HAQ)c | 2.0 | 1.9 | 1.9 | 1.5* | 1.5 | 1.3 | 1.5 | 0.8*
CRP (mg/dL) | 3.9 | 4.3 | 4.6 | 1.8* | 1.0 | 0.9 | 1.0 | 0.4*
a40 mg adalimumab administered every other week
bVisual analogue scale; 0 = best, 10 = worst
cDisability Index of the Health Assessment Questionnaire; 0 = best, 3 = worst, measures the patient’s ability to perform the following: dress/groom, arise, eat, walk, reach, grip, maintain hygiene, and maintain daily activity
*p<0.001, adalimumab vs. placebo, based on mean change from baseline

The time course of ACR 20 response for Study RA-III is shown in Figure 1.

In Study RA-III, 85% of subjects with ACR 20 responses at week 24 maintained the response at 52 weeks. The time course of ACR 20 response for Study RA-I and Study RA-II were similar.

Figure 1. Study RA-III ACR 20 Responses over 52 Weeks

In Study RA-IV, 53% of subjects treated with adalimumab 40 mg every other week plus standard of care had an ACR 20 response at week 24 compared to 35% on placebo plus standard of care (p<0.001). No unique adverse reactions related to the combination of adalimumab and other DMARDs were observed.

In Study RA-V with MTX naïve subjects with recent onset RA, the combination treatment with adalimumab plus MTX led to greater percentages of subjects achieving ACR responses than either MTX monotherapy or adalimumab monotherapy at Week 52 and responses were sustained at Week 104 (see Table 5).

Table 5. ACR Response in Study RA-V (Percent of Subjects)
Response | MTXb; N=257 | Adalimumabc; N=274 | Adalimumab/MTX; N=268
ACR20; Week 52; Week 104 | 63%; 56% | 54%; 49% | 73%; 69%
ACR50; Week 52; Week 104 | 46%; 43% | 41%; 37% | 62%; 59%
ACR70; Week 52; Week 104 | 27%; 28% | 26%; 28% | 46%; 47%
Major Clinical Responsea | 28% | 25% | 49%
aMajor clinical response is defined as achieving an ACR70 response for a continuous six month period
bp<0.05, adalimumab/MTX vs. MTX for ACR 20
p<0.001, adalimumab/MTX vs. MTX for ACR 50 and 70, and Major Clinical Response
cp<0.001, adalimumab/MTX vs. adalimumab

At Week 52, all individual components of the ACR response criteria for Study RA-V improved in the adalimumab/MTX group and improvements were maintained to Week 104.

Radiographic Response

In Study RA-III, structural joint damage was assessed radiographically and expressed as change in Total Sharp Score (TSS) and its components, the erosion score and Joint Space Narrowing (JSN) score, at month 12 compared to baseline. At baseline, the median TSS was approximately 55 in the placebo and 40 mg every other week groups. The results are shown in Table 6. Adalimumab/MTX treated subjects demonstrated less radiographic progression than subjects receiving MTX alone at 52 weeks.

Table 6. Radiographic Mean Changes Over 12 Months in Study RA-III
 | Placebo/MTX | Adalimumab/MTX; 40 mg every other week | Placebo/MTX-; Adalimumab/MTX; (95% Confidence Interval*) | P-value**
Total Sharp score | 2.7 | 0.1 | 2.6 (1.4, 3.8) | <0.001
Erosion score | 1.6 | 0.0 | 1.6 (0.9, 2.2) | <0.001
JSN score | 1.0 | 0.1 | 0.9 (0.3, 1.4) | 0.002
*95% confidence intervals for the differences in change scores between MTX and adalimumab.
**Based on rank analysis

In the open-label extension of Study RA-III, 77% of the original subjects treated with any dose of adalimumab were evaluated radiographically at 2 years. Subjects maintained inhibition of structural damage, as measured by the TSS. Fifty-four percent had no progression of structural damage as defined by a change in the TSS of zero or less. Fifty-five percent (55%) of subjects originally treated with 40 mg adalimumab every other week have been evaluated radiographically at 5 years. Subjects had continued inhibition of structural damage with 50% showing no progression of structural damage defined by a change in the TSS of zero or less.

In Study RA-V, structural joint damage was assessed as in Study RA-III. Greater inhibition of radiographic progression, as assessed by changes in TSS, erosion score and JSN was observed in the adalimumab/MTX combination group as compared to either the MTX or adalimumab monotherapy group at Week 52 as well as at Week 104 (see Table 7).

Table 7. Radiographic Mean Change* in Study RA-V
 |  | MTXa; N=257 | Adalimumaba,b; N=274 | Adalimumab/MTX; N=268
52 Weeks | Total Sharp score | 5.7 (4.2, 7.3) | 3.0 (1.7, 4.3) | 1.3 (0.5, 2.1)
 | Erosion score | 3.7 (2.7, 4.8) | 1.7 (1.0, 2.4) | 0.8 (0.4, 1.2)
 | JSN score | 2.0 (1.2, 2.8) | 1.3 (0.5, 2.1) | 0.5 (0.0, 1.0)
104 Weeks | Total Sharp score | 10.4 (7.7, 13.2) | 5.5 (3.6, 7.4) | 1.9 (0.9, 2.9)
 | Erosion score | 6.4 (4.6, 8.2) | 3.0 (2.0, 4.0) | 1.0 (0.4, 1.6)
 | JSN score | 4.1 (2.7, 5.4) | 2.6 (1.5, 3.7) | 0.9 (0.3, 1.5)
*mean (95% confidence interval)
ap<0.001, adalimumab/MTX vs. MTX at 52 and 104 weeks and for adalimumab/MTX vs. adalimumab at 104 weeks
bp<0.01, for adalimumab/MTX vs. adalimumab at 52 weeks

Physical Function Response

In studies RA-I through IV, adalimumab showed significantly greater improvement than placebo in the disability index of Health Assessment Questionnaire (HAQ-DI) from baseline to the end of study, and significantly greater improvement than placebo in the health-outcomes as assessed by the Short Form Health Survey (SF 36). Improvement was seen in both the Physical Component Summary (PCS) and the Mental Component Summary (MCS).

In Study RA-III, the mean (95% CI) improvement in HAQ-DI from baseline at week 52 was 0.60 (0.55, 0.65) for the adalimumab subjects and 0.25 (0.17, 0.33) for placebo/MTX (p<0.001) subjects. Sixty-three percent of adalimumab-treated subjects achieved a 0.5 or greater improvement in HAQ-DI at week 52 in the double-blind portion of the study. Eighty-two percent of these subjects maintained that improvement through week 104 and a similar proportion of subjects maintained this response through week 260 (5 years) of open-label treatment. Mean improvement in the SF-36 was maintained through the end of measurement at week 156 (3 years).

In Study RA-V, the HAQ-DI and the physical component of the SF-36 showed greater improvement (p<0.001) for the adalimumab/MTX combination therapy group versus either the MTX monotherapy or the adalimumab monotherapy group at Week 52, which was maintained through Week 104.

14.2 Clinical Studies in Juvenile Idiopathic Arthritis

The safety and efficacy of adalimumab was assessed in two studies (Studies JIA-I and JIA-II) in subjects with active polyarticular juvenile idiopathic arthritis (JIA).

Study JIA-I

The safety and efficacy of adalimumab were assessed in a multicenter, randomized, withdrawal, double-blind, parallel-group study in 171 subjects who were 4 to 17 years of age with polyarticular JIA. In the study, the subjects were stratified into two groups: MTX-treated or non-MTX-treated. All subjects had to show signs of active moderate or severe disease despite previous treatment with NSAIDs, analgesics, corticosteroids, or DMARDS. Subjects who received prior treatment with any biologic DMARDS were excluded from the study.

The study included four phases: an open-label lead in phase (OL-LI; 16 weeks), a double-blind randomized withdrawal phase (DB; 32 weeks), an open-label extension phase (OLE-BSA; up to 136 weeks), and an open-label fixed dose phase (OLE-FD; 16 weeks). In the first three phases of the study, adalimumab was administered based on body surface area at a dose of 24 mg/m^2 up to a maximum total body dose of 40 mg subcutaneously (SC) every other week. In the OLE-FD phase, the subjects were treated with 20 mg of adalimumab SC every other week if their weight was less than 30 kg and with 40 mg of adalimumab SC every other week if their weight was 30 kg or greater. Subjects remained on stable doses of NSAIDs and or prednisone (≤0.2 mg/kg/day or 10 mg/day maximum).

Subjects demonstrating a Pediatric ACR 30 response at the end of OL-LI phase were randomized into the double blind (DB) phase of the study and received either adalimumab or placebo every other week for 32 weeks or until disease flare. Disease flare was defined as a worsening of ≥30% from baseline in ≥3 of 6 Pediatric ACR core criteria, ≥2 active joints, and improvement of >30% in no more than 1 of the 6 criteria. After 32 weeks or at the time of disease flare during the DB phase, subjects were treated in the open-label extension phase based on the BSA regimen (OLE-BSA), before converting to a fixed dose regimen based on body weight (OLE-FD phase).

Study JIA-I Clinical Response

At the end of the 16-week OL-LI phase, 94% of the subjects in the MTX stratum and 74% of the subjects in the non-MTX stratum were Pediatric ACR 30 responders. In the DB phase significantly fewer subjects who received adalimumab experienced disease flare compared to placebo, both without MTX (43% vs. 71%) and with MTX (37% vs. 65%). More subjects treated with adalimumab continued to show pediatric ACR 30/50/70 responses at Week 48 compared to subjects treated with placebo. Pediatric ACR responses were maintained for up to two years in the OLE phase in subjects who received adalimumab throughout the study.

Study JIA-II

Adalimumab was assessed in an open-label, multicenter study in 32 subjects who were 2 to <4 years of age or 4 years of age and older weighing <15 kg with moderately to severely active polyarticular JIA. Most subjects (97%) received at least 24 weeks of adalimumab treatment dosed 24 mg/m^2 up to a maximum of 20 mg every other week as a single SC injection up to a maximum of 120 weeks duration. During the study, most subjects used concomitant MTX, with fewer reporting use of corticosteroids or NSAIDs. The primary objective of the study was evaluation of safety [see Adverse Reactions (6.1)].

14.3 Clinical Studies in Psoriatic Arthritis

The safety and efficacy of adalimumab was assessed in two randomized, double-blind, placebo controlled studies in 413 subjects with psoriatic arthritis (PsA). Upon completion of both studies, 383 subjects enrolled in an open-label extension study, in which 40 mg adalimumab was administered every other week.

Study PsA-I enrolled 313 adult subjects with moderately to severely active PsA (>3 swollen and >3 tender joints) who had an inadequate response to NSAID therapy in one of the following forms: (1) distal interphalangeal (DIP) involvement (N=23); (2) polyarticular arthritis (absence of rheumatoid nodules and presence of plaque psoriasis) (N=210); (3) arthritis mutilans (N=1); (4) asymmetric PsA (N=77); or (5) AS-like (N=2). Subjects on MTX therapy (158 of 313 subjects) at enrollment (stable dose of ≤30 mg/week for >1 month) could continue MTX at the same dose. Doses of adalimumab 40 mg or placebo every other week were administered during the 24-week double-blind period of the study.

Compared to placebo, treatment with adalimumab resulted in improvements in the measures of disease activity (see Tables 8 and 9). Among subjects with PsA who received adalimumab, the clinical responses were apparent in some subjects at the time of the first visit (two weeks) and were maintained up to 88 weeks in the ongoing open-label study. Similar responses were seen in subjects with each of the subtypes of psoriatic arthritis, although few subjects were enrolled with the arthritis mutilans and ankylosing spondylitis-like subtypes. Responses were similar in subjects who were or were not receiving concomitant MTX therapy at baseline.

Subjects with psoriatic involvement of at least three percent body surface area (BSA) were evaluated for Psoriatic Area and Severity Index (PASI) responses. At 24 weeks, the proportions of subjects achieving a 75% or 90% improvement in the PASI were 59% and 42% respectively, in the adalimumab group (N=69), compared to 1% and 0% respectively, in the placebo group (N=69) (p<0.001). PASI responses were apparent in some subjects at the time of the first visit (two weeks). Responses were similar in subjects who were or were not receiving concomitant MTX therapy at baseline.

Table 8. ACR Response in Study PsA-I (Percent of Subjects)
 |  | Placebo; N=162 | Adalimumab*; N=151
ACR20
 | Week 12 | 14% | 58%
 | Week 24 | 15% | 57%
ACR50
 | Week 12 | 4% | 36%
 | Week 24 | 6% | 39%
ACR70
 | Week 12 | 1% | 20%
 | Week 24 | 1% | 23%
*p<0.001 for all comparisons between adalimumab and placebo

Table 9. Components of Disease Activity in Study PsA-I
 | Placebo; N=162 |  | Adalimumab*; N=151
Parameter: median | Baseline | 24 weeks | Baseline | 24 weeks
Number of tender jointsa | 23.0 | 17.0 | 20.0 | 5.0
Number of swollen jointsb | 11.0 | 9.0 | 11.0 | 3.0
Physician global assessmentc | 53.0 | 49.0 | 55.0 | 16.0
Patient global assessmentc | 49.5 | 49.0 | 48.0 | 20.0
Painc | 49.0 | 49.0 | 54.0 | 20.0
Disability index (HAQ)d | 1.0 | 0.9 | 1.0 | 0.4
CRP (mg/dL)e | 0.8 | 0.7 | 0.8 | 0.2
* p<0.001 for adalimumab vs. placebo comparisons based on median changes
aScale 0 to 78
bScale 0 to 76
cVisual analog scale; 0=best, 100=worst
dDisability Index of the Health Assessment Questionnaire; 0=best, 3=worst; measures the patient’s ability to perform the following: dress/groom, arise, eat, walk, reach, grip, maintain hygiene, and maintain daily activity.
eNormal range: 0 to 0.287 mg/dL

Similar results were seen in an additional, 12-week study in 100 subjects with moderate to severe psoriatic arthritis who had suboptimal response to DMARD therapy as manifested by ≥3 tender joints and ≥3 swollen joints at enrollment.

Radiographic Response

Radiographic changes were assessed in the PsA studies. Radiographs of hands, wrists, and feet were obtained at baseline and Week 24 during the double-blind period when subjects were on adalimumab or placebo and at Week 48 when all subjects were on open-label adalimumab. A modified Total Sharp Score (mTSS), which included distal interphalangeal joints (i.e., not identical to the TSS used for rheumatoid arthritis), was used by readers blinded to treatment group to assess the radiographs.

Adalimumab-treated subjects demonstrated greater inhibition of radiographic progression compared to placebo-treated subjects and this effect was maintained at 48 weeks (see Table 10).

Table 10. Change in Modified Total Sharp Score in Psoriatic Arthritis
 | Placebo; N=141 | Adalimumab; N=133
 | Week 24 | Week 24 | Week 48
Baseline mean | 22.1 | 23.4 | 23.4
Mean Change ± SD | 0.9 ± 3.1 | -0.1 ± 1.7 | -0.2 ± 4.9*
*<0.001 for the difference between adalimumab, Week 48 and Placebo, Week 24 (primary analysis)

Physical Function Response

In Study PsA-I, physical function and disability were assessed using the HAQ Disability Index (HAQ-DI) and the SF-36 Health Survey. Subjects treated with 40 mg of adalimumab every other week showed greater improvement from baseline in the HAQ-DI score (mean decreases of 47% and 49% at Weeks 12 and 24 respectively) in comparison to placebo (mean decreases of 1% and 3% at Weeks 12 and 24 respectively). At Weeks 12 and 24, subjects treated with adalimumab showed greater improvement from baseline in the SF-36 Physical Component Summary score compared to subjects treated with placebo, and no worsening in the SF-36 Mental Component Summary score. Improvement in physical function based on the HAQ-DI was maintained for up to 84 weeks through the open-label portion of the study.

14.4 Clinical Studies in Ankylosing Spondylitis

The safety and efficacy of adalimumab 40 mg every other week was assessed in 315 adult subjects in a randomized, 24 week double-blind, placebo-controlled study in subjects with active ankylosing spondylitis (AS) who had an inadequate response to glucocorticoids, NSAIDs, analgesics, methotrexate or sulfasalazine. Active AS was defined as subjects who fulfilled at least two of the following three criteria: (1) a Bath AS disease activity index (BASDAI) score ≥4 cm, (2) a visual analog score (VAS) for total back pain ≥40 mm, and (3) morning stiffness ≥1 hour. The blinded period was followed by an open-label period during which subjects received adalimumab 40 mg every other week subcutaneously for up to an additional 28 weeks.

Improvement in measures of disease activity was first observed at Week 2 and maintained through 24 weeks as shown in Figure 2 and Table 11.

Responses of subjects with total spinal ankylosis (n=11) were similar to those without total ankylosis.

Figure 2. ASAS 20 Response By Visit, Study AS-I

At 12 weeks, the ASAS 20/50/70 responses were achieved by 58%, 38%, and 23%, respectively, of subjects receiving adalimumab, compared to 21%, 10%, and 5% respectively, of subjects receiving placebo (p<0.001). Similar responses were seen at Week 24 and were sustained in subjects receiving open-label adalimumab for up to 52 weeks.

A greater proportion of subjects treated with adalimumab (22%) achieved a low level of disease activity at 24 weeks (defined as a value <20 [on a scale of 0 to 100 mm] in each of the four ASAS response parameters) compared to subjects treated with placebo (6%).

Table 11. Components of Ankylosing Spondylitis Disease Activity
 | Placebo; N=107 |  | Adalimumab; N=208
 | Baseline; mean | Week 24; mean | Baseline; mean | Week 24; mean
ASAS 20 Response Criteria*
Patient’s Global Assessment of Disease Activitya* | 65 | 60 | 63 | 38
Total back pain* | 67 | 58 | 65 | 37
Inflammationb* | 6.7 | 5.6 | 6.7 | 3.6
BASFIc* | 56 | 51 | 52 | 34
BASDAId score* | 6.3 | 5.5 | 6.3 | 3.7
BASMIe score* | 4.2 | 4.1 | 3.8 | 3.3
Tragus to wall (cm) | 15.9 | 15.8 | 15.8 | 15.4
Lumbar flexion (cm) | 4.1 | 4.0 | 4.2 | 4.4
Cervical rotation (degrees) | 42.2 | 42.1 | 48.4 | 51.6
Lumbar side flexion (cm) | 8.9 | 9.0 | 9.7 | 11.7
Intermalleolar distance (cm) | 92.9 | 94.0 | 93.5 | 100.8
CRPf* | 2.2 | 2.0 | 1.8 | 0.6
aPercent of subjects with at least a 20% and 10-unit improvement measured on a Visual Analog Scale (VAS) with 0 = “none” and 100 = “severe”
bMean of questions 5 and 6 of BASDAI (defined in ‘d’)
cBath Ankylosing Spondylitis Functional Index
dBath Ankylosing Spondylitis Disease Activity Index
eBath Ankylosing Spondylitis Metrology Index
fC-Reactive Protein (mg/dL)
*Statistically significant for comparisons between adalimumab and placebo at Week 24

A second randomized, multicenter, double-blind, placebo-controlled study of 82 subjects with ankylosing spondylitis showed similar results.

Subjects treated with adalimumab achieved improvement from baseline in the Ankylosing Spondylitis Quality of Life Questionnaire (ASQoL) score (-3.6 vs. -1.1) and in the Short Form Health Survey (SF-36) Physical Component Summary (PCS) score (7.4 vs. 1.9) compared to placebo-treated subjects at Week 24.

14.5 Clinical Studies in Adults with Crohn’s Disease

The safety and efficacy of multiple doses of adalimumab were assessed in adult subjects with moderately to severely active Crohn’s disease, CD, (Crohn’s Disease Activity Index (CDAI) ≥220 and ≤450) in randomized, double-blind, placebo-controlled studies. Concomitant stable doses of aminosalicylates, corticosteroids, and/or immunomodulatory agents were permitted, and 79% of subjects continued to receive at least one of these medications.

Induction of clinical remission (defined as CDAI <150) was evaluated in two studies. In Study CD-I, 299 TNF-blocker naïve subjects were randomized to one of four treatment groups: the placebo group received placebo at Weeks 0 and 2, the 160/80 group received 160 mg adalimumab at Week 0 and 80 mg at Week 2, the 80/40 group received 80 mg at Week 0 and 40 mg at Week 2, and the 40/20 group received 40 mg at Week 0 and 20 mg at Week 2. Clinical results were assessed at Week 4.

In the second induction study, Study CD-II, 325 subjects who had lost response to, or were intolerant to, previous infliximab therapy were randomized to receive either 160 mg adalimumab at Week 0 and 80 mg at Week 2, or placebo at Weeks 0 and 2. Clinical results were assessed at Week 4.

Maintenance of clinical remission was evaluated in Study CD-III. In this study, 854 subjects with active disease received open-label adalimumab, 80 mg at week 0 and 40 mg at Week 2. Subjects were then randomized at Week 4 to 40 mg adalimumab every other week, 40 mg adalimumab every week, or placebo. The total study duration was 56 weeks. Subjects in clinical response (decrease in CDAI ≥70) at Week 4 were stratified and analyzed separately from those not in clinical response at Week 4.

Induction of Clinical Remission

A greater percentage of the subjects treated with 160/80 mg adalimumab achieved induction of clinical remission versus placebo at Week 4 regardless of whether the subjects were TNF blocker naïve (CD-I), or had lost response to or were intolerant to infliximab (CD-II) (see Table 12).

Table 12. Induction of Clinical Remission in Studies CD-I and CD-II (Percent of Subjects)
 | CD-I |  | CD-II
 | Placebo N=74 | Adalimumab; 160/80 mg; N=76 | Placebo N=166 | Adalimumab; 160/80 mg; N=159
Week 4
Clinical remission | 12% | 36%* | 7% | 21%*
Clinical response | 34% | 58%** | 34% | 52%**
Clinical remission is CDAI score < 150; clinical response is decrease in CDAI of at least 70 points.
*p<0.001 for adalimumab vs. placebo pairwise comparison of proportions
**p<0.01 for adalimumab vs. placebo pairwise comparison of proportions

Maintenance of Clinical Remission

In Study CD-III at Week 4, 58% (499/854) of subjects were in clinical response and were assessed in the primary analysis. At Weeks 26 and 56, greater proportions of subjects who were in clinical response at Week 4 achieved clinical remission in the adalimumab 40 mg every other week maintenance group compared to subjects in the placebo maintenance group (see Table 13). The group that received adalimumab therapy every week did not demonstrate significantly higher remission rates compared to the group that received adalimumab every other week.

Table 13. Maintenance of Clinical Remission in CD-III (Percent of Subjects)
 | Placebo | 40 mg Adalimumab every other week
 | N=170 | N=172
Week 26
Clinical remission | 17% | 40%*
Clinical response | 28% | 54%*
Week 56
Clinical remission | 12% | 36%*
Clinical response | 18% | 43%*
Clinical remission is CDAI score <150; clinical response is decrease in CDAI of at least 70 points.
*p<0.001 for adalimumab vs. placebo pairwise comparisons of proportions

Of those in response at Week 4 who attained remission during the study, subjects in the adalimumab every other week group maintained remission for a longer time than subjects in the placebo maintenance group. Among subjects who were not in response by Week 12, therapy continued beyond 12 weeks did not result in significantly more responses.

14.6 Clinical Studies in Pediatric Subjects with Crohn’s Disease

A randomized, double-blind, 52-week clinical study of 2 dose concentrations of adalimumab (Study PCD-I) was conducted in 192 pediatric subjects (6 to 17 years of age) with moderately to severely active Crohn’s disease (defined as Pediatric Crohn’s Disease Activity Index (PCDAI) score >30). Enrolled subjects had over the previous two year period an inadequate response to corticosteroids or an immunomodulator (i.e., azathioprine, 6-mercaptopurine, or methotrexate). Subjects who had previously received a TNF blocker were allowed to enroll if they had previously had loss of response or intolerance to that TNF blocker.

Subjects received open-label induction therapy at a dose based on their body weight (≥40 kg and <40 kg). Subjects weighing ≥40 kg received 160 mg (at Week 0) and 80 mg (at Week 2). Subjects weighing <40 kg received 80 mg (at Week 0) and 40 mg (at Week 2). At Week 4, subjects within each body weight category (≥40 kg and <40 kg) were randomized 1:1 to one of two maintenance dose regimens (high dose and low dose). The high dose was 40 mg every other week for subjects weighing ≥40 kg and 20 mg every other week for subjects weighing <40 kg. The low dose was 20 mg every other week for subjects weighing ≥40 kg and 10 mg every other week for subjects weighing <40 kg.

Concomitant stable dosages of corticosteroids (prednisone dosage ≤40 mg/day or equivalent) and immunomodulators (azathioprine, 6-mercaptopurine, or methotrexate) were permitted throughout the study.

At Week 12, subjects who experienced a disease flare (increase in PCDAI of ≥15 from Week 4 and absolute PCDAI >30) or who were non-responders (did not achieve a decrease in the PCDAI of ≥15 from baseline for 2 consecutive visits at least 2 weeks apart) were allowed to dose-escalate (i.e., switch from blinded every other week dosing to blinded every week dosing); subjects who dose-escalated were considered treatment failures.

At baseline, 38% of subjects were receiving corticosteroids, and 62% of subjects were receiving an immunomodulator. Forty-four percent (44%) of subjects had previously lost response or were intolerant to a TNF blocker. The median baseline PCDAI score was 40.

Of the 192 subjects total, 188 subjects completed the 4 week induction period, 152 subjects completed 26 weeks of treatment, and 124 subjects completed 52 weeks of treatment. Fifty-one percent (51%) (48/95) of subjects in the low maintenance dose group dose-escalated, and 38% (35/93) of subjects in the high maintenance dose group dose-escalated.

At Week 4, 28% (52/188) of subjects were in clinical remission (defined as PCDAI ≤10).

The proportions of subjects in clinical remission (defined as PCDAI ≤10) and clinical response (defined as reduction in PCDAI of at least 15 points from baseline) were assessed at Weeks 26 and 52.

At both Weeks 26 and 52, the proportion of subjects in clinical remission and clinical response was numerically higher in the high dose group compared to the low dose group (Table 14). The recommended maintenance regimen is 20 mg every other week for subjects weighing <40 kg and 40 mg every other week for subjects weighing ≥40 kg. Every week dosing is not the recommended maintenance dosing regimen [see Dosage and Administration (2.3)].

Table 14. Clinical Remission and Clinical Response in Study PCD-1
 | Low Maintenance Dose†; (20 or 10 mg every other week); N = 95 | High Maintenance Dose#; (40 or 20 mg every other week); N = 93
Week 26
Clinical Remission‡ | 28% | 39%
Clinical Response§ | 48% | 59%
Week 52
Clinical Remission‡ | 23% | 33%
Clinical Response§ | 28% | 42%
†The low maintenance dose was 20 mg every other week for subjects weighing ≥40 kg and 10 mg every other week for subjects weighing <40 kg.
#The high maintenance dose was 40 mg every other week for subjects weighing ≥40 kg and 20 mg every other week for subjects weighing <40 kg.
‡Clinical remission defined as PCDAI ≤10.
§Clinical response defined as reduction in PCDAI of at least 15 points from baseline.

14.7 Clinical Studies in Adults with Ulcerative Colitis

The safety and efficacy of adalimumab were assessed in adult subjects with moderately to severely active ulcerative colitis (Mayo score 6 to 12 on a 12 point scale, with an endoscopy subscore of 2 to 3 on a scale of 0 to 3) despite concurrent or prior treatment with immunosuppressants such as corticosteroids, azathioprine, or 6-MP in two randomized, double-blind, placebo-controlled clinical studies (Studies UC-I and UC-II). Both studies enrolled TNF-blocker naïve subjects, but Study UC-II also allowed entry of subjects who lost response to or were intolerant to TNF-blockers. Forty percent (40%) of subjects enrolled in Study UC-II had previously used another TNF-blocker.

Concomitant stable doses of aminosalicylates and immunosuppressants were permitted. In Studies UC-I and II, subjects were receiving aminosalicylates (69%), corticosteroids (59%) and/or azathioprine or 6-MP (37%) at baseline. In both studies, 92% of subjects received at least one of these medications.

Induction of clinical remission (defined as Mayo score ≤2 with no individual subscores >1) at Week 8 was evaluated in both studies. Clinical remission at Week 52 and sustained clinical remission (defined as clinical remission at both Weeks 8 and 52) were evaluated in Study UC-II.

In Study UC-I, 390 TNF-blocker naïve subjects were randomized to one of three treatment groups for the primary efficacy analysis. The placebo group received placebo at Weeks 0, 2, 4 and 6. The 160/80 group received 160 mg adalimumab at Week 0 and 80 mg at Week 2, and the 80/40 group received 80 mg adalimumab at Week 0 and 40 mg at Week 2. After Week 2, subjects in both adalimumab treatment groups received 40 mg every other week.

In Study UC-II, 518 subjects were randomized to receive either adalimumab 160 mg at Week 0, 80 mg at Week 2, and 40 mg every other week starting at Week 4 through Week 50, or placebo starting at Week 0 and every other week through Week 50. Corticosteroid taper was permitted starting at Week 8.

In both Studies UC-I and UC-II, a greater percentage of the subjects treated with 160/80 mg of adalimumab compared to subjects treated with placebo achieved induction of clinical remission. In Study UC-II, a greater percentage of the subjects treated with 160/80 mg of adalimumab compared to subjects treated with placebo achieved sustained clinical remission (clinical remission at both Weeks 8 and 52) (Table 15).

Table 15. Induction of Clinical Remission in Studies UC-I and UC-II and Sustained Clinical Remission in Study UC-II (Percent of Subjects)
 | Study UC-I |  |  | Study UC-II
 | Placebo N=130 | Adalimumab 160/80 mg N=130 | Treatment Difference (95% CI) | Placebo N=246 | Adalimumab 160/80 mg N=248 | Treatment Difference (95% CI)
Induction of Clinical Remission (Clinical Remission at Week 8) | 9.2% | 18.5% | 9.3%*; (0.9%, 17.6%) | 9.3% | 16.5% | 7.2%*; (1.2%, 12.9%)
Sustained Clinical Remission (Clinical Remission at both Weeks 8 and 52) | N/A | N/A | N/A | 4.1% | 8.5% | 4.4%*; (0.1%, 8.6%)
Clinical remission is defined as Mayo score ≤2 with no individual subscores >1. CI=Confidence interval
*p<0.05 for adalimumab vs. placebo pairwise comparison of proportions

In Study UC-I, there was no statistically significant difference in clinical remission observed between the adalimumab 80/40 mg group and the placebo group at Week 8.

In Study UC-II, 17.3% (43/248) in the adalimumab group were in clinical remission at Week 52 compared to 8.5% (21/246) in the placebo group (treatment difference: 8.8%; 95% confidence interval (CI): [2.8%, 14.5%]; p<0.05).

In the subgroup of subjects in Study UC-II with prior TNF-blocker use, the treatment difference for induction of clinical remission appeared to be lower than that seen in the whole study population, and the treatment differences for sustained clinical remission and clinical remission at Week 52 appeared to be similar to those seen in the whole study population. The subgroup of subjects with prior TNF-blocker use achieved induction of clinical remission at 9% (9/98) in the adalimumab group versus 7% (7/101) in the placebo group, and sustained clinical remission at 5% (5/98) in the adalimumab group versus 1% (1/101) in the placebo group. In the subgroup of subjects with prior TNF-blocker use, 10% (10/98) were in clinical remission at Week 52 in the adalimumab group versus 3% (3/101) in the placebo group.

14.8 Clinical Studies in Plaque Psoriasis

The safety and efficacy of adalimumab were assessed in randomized, double-blind, placebo-controlled studies in 1696 adult subjects with moderate to severe chronic plaque psoriasis (Ps) who were candidates for systemic therapy or phototherapy.

Study Ps-I evaluated 1212 subjects with chronic Ps with ≥10% body surface area (BSA) involvement, Physician’s Global Assessment (PGA) of at least moderate disease severity, and Psoriasis Area and Severity Index (PASI) ≥12 within three treatment periods. In period A, subjects received placebo or adalimumab at an initial dose of 80 mg at Week 0 followed by a dose of 40 mg every other week starting at Week 1. After 16 weeks of therapy, subjects who achieved at least a PASI 75 response at Week 16, defined as a PASI score improvement of at least 75% relative to baseline, entered period B and received open-label 40 mg adalimumab every other week. After 17 weeks of open label therapy, subjects who maintained at least a PASI 75 response at Week 33 and were originally randomized to active therapy in period A were re-randomized in period C to receive 40 mg adalimumab every other week or placebo for an additional 19 weeks. Across all treatment groups the mean baseline PASI score was 19 and the baseline Physician’s Global Assessment score ranged from “moderate” (53%) to “severe” (41%) to “very severe” (6%).

Study Ps-II evaluated 99 subjects randomized to adalimumab and 48 subjects randomized to placebo with chronic plaque psoriasis with ≥10% BSA involvement and PASI ≥12. Subjects received placebo, or an initial dose of 80 mg adalimumab at Week 0 followed by 40 mg every other week starting at Week 1 for 16 weeks. Across all treatment groups the mean baseline PASI score was 21 and the baseline PGA score ranged from “moderate” (41%) to “severe” (51%) to “very severe” (8%).

Studies Ps-I and II evaluated the proportion of subjects who achieved “clear” or “minimal” disease on the 6-point PGA scale and the proportion of subjects who achieved a reduction in PASI score of at least 75% (PASI 75) from baseline at Week 16 (see Table 16 and 17).

Additionally, Study Ps-I evaluated the proportion of subjects who maintained a PGA of “clear” or “minimal” disease or a PASI 75 response after Week 33 and on or before Week 52.

Table 16. Efficacy Results at 16 Weeks in Study Ps-I Number of Subjects (%)
 | Adalimumab 40 mg; every other week | Placebo
 | N=814 | N=398
PGA: Clear or minimal* | 506 (62%) | 17 (4%)
PASI 75 | 578 (71%) | 26 (7%)
*Clear = no plaque elevation, no scale, plus or minus hyperpigmentation or diffuse pink or red coloration
Minimal = possible but difficult to ascertain whether there is slight elevation of plaque above normal skin, plus or minus surface dryness with some white coloration, plus or minus up to red coloration

Table 17. Efficacy Results at 16 Weeks in Study Ps-II Number of Subjects (%)
 | Adalimumab 40 mg; every other week | Placebo
 | N=99 | N=48
PGA: Clear or minimal* | 70 (71%) | 5 (10%)
PASI 75 | 77 (78%) | 9 (19%)
*Clear = no plaque elevation, no scale, plus or minus hyperpigmentation or diffuse pink or red coloration Minimal = possible but difficult to ascertain whether there is slight elevation of plaque above normal skin, plus or minus surface dryness with some white coloration, plus or minus up to red coloration

Additionally, in Study Ps-I, subjects on adalimumab who maintained a PASI 75 were re-randomized to adalimumab (N = 250) or placebo (N = 240) at Week 33. After 52 weeks of treatment with adalimumab, more subjects on adalimumab maintained efficacy when compared to subjects who were re-randomized to placebo based on maintenance of PGA of “clear” or “minimal” disease (68% vs. 28%) or a PASI 75 (79% vs. 43%).

A total of 347 stable responders participated in a withdrawal and retreatment evaluation in an open-label extension study. Median time to relapse (decline to PGA “moderate” or worse) was approximately 5 months. During the withdrawal period, no subject experienced transformation to either pustular or erythrodermic psoriasis. A total of 178 subjects who relapsed re-initiated treatment with 80 mg of adalimumab, then 40 mg every other week beginning at week 1. At week 16, 69% (123/178) of subjects had a response of PGA “clear” or “minimal”.

A randomized, double-blind study (Study Ps-III) compared the efficacy and safety of adalimumab versus placebo in 217 adult subjects. Subjects in the study had to have chronic plaque psoriasis of at least moderate severity on the PGA scale, fingernail involvement of at least moderate severity on a 5-point Physician’s Global Assessment of Fingernail Psoriasis (PGA-F) scale, a Modified Nail Psoriasis Severity Index (mNAPSI) score for the target-fingernail of ≥8, and either a BSA involvement of at least 10% or a BSA involvement of at least 5% with a total mNAPSI score for all fingernails of ≥20. Subjects received an initial dose of 80 mg adalimumab followed by 40 mg every other week (starting one week after the initial dose) or placebo for 26 weeks followed by open-label adalimumab treatment for an additional 26 weeks. This study evaluated the proportion of subjects who achieved “clear” or “minimal” assessment with at least a 2-grade improvement on the PGA-F scale and the proportion of subjects who achieved at least a 75% improvement from baseline in the mNAPSI score (mNAPSI 75) at Week 26.

At Week 26, a higher proportion of subjects in the adalimumab group than in the placebo group achieved the PGA-F endpoint. Furthermore, a higher proportion of subjects in the adalimumab group than in the placebo group achieved mNAPSI 75 at Week 26 (see Table 18).

Table 18. Efficacy Results at 26 Weeks
Endpoint | Adalimumab 40 mg; every other week*; N=109 | Placebo; N=108
PGA-F: ≥2-grade improvement and clear or minimal | 49% | 7%
mNAPSI 75 | 47% | 3%
*Subjects received 80 mg of adalimumab at Week 0, followed by 40 mg every other week starting at Week 1.

Nail pain was also evaluated and improvement in nail pain was observed in Study Ps-III.

14.9 Clinical Studies in Hidradenitis Suppurativa

Two randomized, double-blind, placebo-controlled studies (Studies HS-I and II) evaluated the safety and efficacy of adalimumab in a total of 633 adult subjects with moderate to severe hidradenitis suppurativa (HS) with Hurley Stage II or III disease and with at least 3 abscesses or inflammatory nodules. In both studies, subjects received placebo or adalimumab at an initial dose of 160 mg at Week 0, 80 mg at Week 2, and 40 mg every week starting at Week 4 and continued through Week 11. Subjects used topical antiseptic wash daily. Concomitant oral antibiotic use was allowed in Study HS-II.

Both studies evaluated Hidradenitis Suppurativa Clinical Response (HiSCR) at Week 12. HiSCR was defined as at least a 50% reduction in total abscess and inflammatory nodule count with no increase in abscess count and no increase in draining fistula count relative to baseline (see Table 19). Reduction in HS-related skin pain was assessed using a Numeric Rating Scale in subjects who entered the study with an initial baseline score of 3 or greater on a 11 point scale.

In both studies, a higher proportion of adalimumab- than placebo-treated subjects achieved HiSCR (see Table 19).

Table 19. Efficacy Results at 12 Weeks in Subjects with Moderate to Severe Hidradenitis Suppurativa
 | HS Study I |  | HS Study II*
 | Placebo | Adalimumab 40 mg Weekly | Placebo | Adalimumab 40 mg Weekly
Hidradenitis; Suppurativa Clinical; Response (HiSCR) | N=154; 40 (26%) | N=153; 64 (42%) | N=163; 45 (28%) | N=163; 96 (59%)
*19.3% of subjects in Study HS-II continued baseline oral antibiotic therapy during the study

In both studies, from Week 12 to Week 35 (Period B), subjects who had received adalimumab were re-randomized to 1 of 3 treatment groups (adalimumab 40 mg every week, adalimumab 40 mg every other week, or placebo). Subjects who had been randomized to placebo were assigned to receive adalimumab 40 mg every week (Study HS-I) or placebo (Study HS-II).

During Period B, flare of HS, defined as ≥25% increase from baseline in abscesses and inflammatory nodule counts and with a minimum of 2 additional lesions, was documented in 22 (22%) of the 100 subjects who were withdrawn from adalimumab treatment following the primary efficacy timepoint in two studies.

14.10 Clinical Studies in Adults with Uveitis

The safety and efficacy of adalimumab were assessed in adult subjects with non-infectious intermediate, posterior and panuveitis excluding subjects with isolated anterior uveitis, in two randomized, double-masked, placebo-controlled studies (UV I and II). Subjects received placebo or adalimumab at an initial dose of 80 mg followed by 40 mg every other week starting one week after the initial dose. The primary efficacy endpoint in both studies was ´time to treatment failure´.

Treatment failure was a multi-component outcome defined as the development of new inflammatory chorioretinal and/or inflammatory retinal vascular lesions, an increase in anterior chamber (AC) cell grade or vitreous haze (VH) grade or a decrease in best corrected visual acuity (BCVA).

Study UV I evaluated 217 subjects with active uveitis while being treated with corticosteroids (oral prednisone at a dose of 10 to 60 mg/day). All subjects received a standardized dose of prednisone 60 mg/day at study entry followed by a mandatory taper schedule, with complete corticosteroid discontinuation by Week 15.

Study UV II evaluated 226 subjects with inactive uveitis while being treated with corticosteroids (oral prednisone 10 to 35 mg/day) at baseline to control their disease. Subjects subsequently underwent a mandatory taper schedule, with complete corticosteroid discontinuation by Week 19.

Clinical Response

Results from both studies demonstrated statistically significant reduction of the risk of treatment failure in subjects treated with adalimumab versus subjects receiving placebo. In both studies, all components of the primary endpoint contributed cumulatively to the overall difference between adalimumab and placebo groups (Table 20).

Table 20. Time to Treatment Failure in Studies UV I and UV II
 | UV I |  |  | UV II
 | Placebo; (N = 107) | Adalimumab; (N = 110) | HR; [95% CI]a | Placebo; (N = 111) | Adalimumab; (N = 115) | HR; [95% CI]a
Failureb n (%) | 84 (78.5) | 60 (54.5) | 0.50; [0.36, 0.70] | 61 (55.0) | 45 (39.1) | 0.57; [0.39, 0.84]
Median Time; to Failure; (Months); [95% CI] | 3.0; [2.7, 3.7] | 5.6; [3.9, 9.2] | N/A | 8.3; [4.8, 12.0] | NEc | N/A
ªHR of Adalimumab versus placebo from proportional hazards regression with treatment as factor.
bTreatment failure at or after Week 6 in Study UV I, or at or after Week 2 in Study UV II, was counted as event. Subjects who discontinued the study were censored at the time of dropping out.
cNE = not estimable. Fewer than half of at-risk subjects had an event.

Figure 3: Kaplan-Meier Curves Summarizing Time to Treatment Failure on or after Week 6 (Study UV I) or Week 2 (Study UV II)

Study UV I

Study UV II

Note: P# = Placebo (Number of Events/Number at Risk); A# = Adalimumab (Number of Events/Number at Risk).

14.11 Clinical Studies in Pediatric Subjects with Uveitis

The safety and efficacy of adalimumab were assessed in a randomized, double-masked, placebo-controlled study of 90 pediatric subjects from 2 to < 18 years of age with active JIA-associated non-infectious uveitis (PUV-I). Subjects received either placebo or 20 mg adalimumab (if < 30 kg) or 40 mg adalimumab (if ≥ 30 kg) every other week in combination with a dose of methotrexate. Concomitant dosages of corticosteroids were permitted at study entry followed by a mandatory reduction in topical corticosteroids within 3 months.

The primary endpoint was ‘time to treatment failure’. The criteria determining treatment failure were worsening or sustained non-improvement in ocular inflammation, or worsening of ocular co-morbidities.

Clinical Response

Adalimumab significantly decreased the risk of treatment failure by 75% relative to placebo (HR = 0.25 [95% CI: 0.12, 0.49]) (Table 21).

Table 21. Analysis Results of Time to Treatment Failure (Study PUV-I)

 |  | Placebo; (N = 30) | Adalimumab; (N = 60) | HR (95% CI)a
Failure (n [%]) |  | 18 (60%) | 16 (26.7%) | 0.25; (0.12, 0.49)
Median Time; to Failure (Weeks); (95% CI)b |  | 24.1; (12.4, 81.0) | NEc

a HR of adalimumab versus placebo from proportional hazards regression with treatment as

factor.

b Estimated based on Kaplan-Meier curve.

c NE = not estimable. Fewer than half of at-risk subjects had an event.

Figure 4: Kaplan-Meier Curves Summarizing Time to Treatment Failure (Study PUV-I)

Study PUV-I

Note: P = Placebo (Number at Risk); H = Adalimumab (Number at Risk).

15 REFERENCES

1. National Cancer Institute. Surveillance, Epidemiology, and End Results Database (SEER) Program. SEER Incidence Crude Rates, 17 Registries, 2000-2007.

16 HOW SUPPLIED/STORAGE AND HANDLING

Adalimumab-ryvk injection is supplied as a preservative-free, sterile, clear and colorless solution for subcutaneous administration. The following packaging configurations are available.

- Adalimumab-ryvk Autoinjector Carton - 40 mg/0.4 mL (Two Count)

Adalimumab-ryvk is supplied in a carton containing two alcohol preps and two dose trays. Each dose tray consists of a single-dose autoinjector, containing a 1 mL prefilled glass syringe with a fixed 29-gauge (1/2 inch) needle, providing 40 mg/0.4 mL of Adalimumab-ryvk. The Adalimumab-ryvk autoinjector is not made with natural rubber latex. The NDC number is NDC 82009-156-22.

- Adalimumab-ryvk Prefilled Syringe Carton - 40 mg/0.4 mL (Two Count)

Adalimumab-ryvk is supplied in a carton containing two alcohol preps and two dose trays. Each dose tray consists of a single-dose, 1 mL prefilled glass syringe with a fixed thin wall, 1/2 inch needle and fitted with a plunger rod, finger grip and a rigid needle cover, providing 40 mg/0.4 mL of Adalimumab-ryvk. The gray needle cover is not made with natural rubber latex. The NDC number is NDC 82009-158-22.

Storage and Stability

Do not use beyond the expiration date on the container. Adalimumab-ryvk must be refrigerated at 36°F to 46°F (2°C to 8°C). DO NOT FREEZE. Do not use if frozen even if it has been thawed.

Store in original carton until time of administration to protect from light.

If needed, for example when traveling, Adalimumab-ryvk may be stored at room temperature up to a maximum of 77°F (25°C) for a period of up to 30 days, with protection from light. Adalimumab-ryvk should be discarded if not used within the 30-day period. Record the date when Adalimumab-ryvk is first removed from the refrigerator in the spaces provided on the carton and dose tray.

Do not store Adalimumab-ryvk in extreme heat or cold.

17 PATIENT COUNSELING INFORMATION

Advise the patient or caregiver to read the FDA-approved patient labeling (Medication Guide and Instructions for Use).

Infections

Inform patients that Adalimumab-ryvk may lower the ability of their immune system to fight infections. Instruct patients of the importance of contacting their doctor if they develop any symptoms of infection, including tuberculosis, invasive fungal infections, and reactivation of hepatitis B virus infections [see Warnings and Precautions (5.1, 5.2, 5.4)].

Malignancies

Counsel patients about the risk of malignancies while receiving Adalimumab-ryvk [see Warnings and Precautions (5.2)].

Hypersensitivity Reactions

Advise patients to seek immediate medical attention if they experience any symptoms of severe hypersensitivity reactions [see Warnings and Precautions (5.3), How Supplied/Storage and Handling (16)].

Other Medical Conditions

Advise patients to report any signs of new or worsening medical conditions such as congestive heart failure, neurological disease, autoimmune disorders, or cytopenias. Advise patients to report any symptoms suggestive of a cytopenia such as bruising, bleeding, or persistent fever [see Warnings and Precautions (5.5, 5.6, 5.8, 5.9)].

Instructions on Injection Technique

Inform patients that the first injection is to be performed under the supervision of a qualified health care professional. If a patient or caregiver is to administer Adalimumab-ryvk, instruct them in injection techniques and assess their ability to inject subcutaneously to ensure the proper administration of Adalimumab-ryvk [see Instructions for Use].

For patients who will use the Adalimumab-ryvk Autoinjector, tell them that they:

- Will hear a ‘1st click’ when the orange needle sleeve is pressed against the injection site. The ‘1st click’ means the start of the injection.
- Must keep holding the Adalimumab-ryvk Autoinjector against their squeezed, raised skin until all of the medicine is injected. This can take up to 15 seconds.
- Will know that the injection has finished when the orange indicator fully appears in the window view, stops moving, and they hear a second ‘click’.

Instruct patients to dispose of their used needles and syringes or used autoinjector in a FDA-cleared sharps disposal container immediately after use. Instruct patients not to dispose of loose needles and syringes or autoinjector in their household trash. Instruct patients that if they do not have a FDA-cleared sharps disposal container, they may use a household container that is made of a heavy-duty plastic, can be closed with a tight-fitting and puncture-resistant lid without sharps being able to come out, upright and stable during use, leak-resistant, and properly labeled to warn of hazardous waste inside the container.

Instruct patients that when their sharps disposal container is almost full, they will need to follow their community guidelines for the correct way to dispose of their sharps disposal container. Instruct patients that there may be state or local laws regarding disposal of used needles and syringes. Refer patients to the FDA’s website at http://www.fda.gov/safesharpsdisposal for more information about safe sharps disposal, and for specific information about sharps disposal in the state that they live in.

Instruct patients not to dispose of their used sharps disposal container in their household trash unless their community guidelines permit this. Instruct patients not to recycle their used sharps disposal container.

Brands listed are the trademarks of their respective owners.

Manufactured By:

Alvotech USA Inc.

Leesburg, VA 20175

U.S. License No. 2225

Manufactured At:

Alvotech Hf, Reykjavik, 102

Product of Iceland

Manufactured For:

Quallent Pharmaceuticals Health LLC

Grand Cayman, Cayman Islands

MEDICATION GUIDE

Adalimumab-ryvk (ada-LIM-u-mab ryvk)

injection, for subcutaneous use

Read the Medication Guide that comes with Adalimumab-ryvk before you start taking it and each time you get a refill. There may be new information. This Medication Guide does not take the place of talking with your doctor about your medical condition or treatment.

What is the most important information I should know about Adalimumab-ryvk?

Adalimumab-ryvk is a medicine that affects your immune system. Adalimumab-ryvk can lower the ability of your immune system to fight infections. Serious infections have happened in people taking adalimumab products. These serious infections include tuberculosis (TB) and infections caused by viruses, fungi or bacteria that have spread throughout the body. Some people have died from these infections.

- Your doctor should test you for TB before starting Adalimumab-ryvk.
- Your doctor should check you closely for signs and symptoms of TB during treatment with Adalimumab-ryvk.

You should not start taking Adalimumab-ryvk if you have any kind of infection unless your doctor says it is okay.

Before starting Adalimumab-ryvk, tell your doctor if you:

- think you have an infection or have symptoms of an infection such as:

- fever, sweats, or chills
- muscle aches
- cough
- shortness of breath
- blood in phlegm

- warm, red, or painful skin or sores on your body
- diarrhea or stomach pain
- burning when you urinate or urinate more often than normal
- feel very tired
- weight loss

- are being treated for an infection.
- get a lot of infections or have infections that keep coming back.
- have diabetes.
- have TB, or have been in close contact with someone with TB.
- were born in, lived in, or traveled to countries where there is more risk for getting TB. Ask your doctor if you are not sure.
- live or have lived in certain parts of the country (such as the Ohio and Mississippi River valleys) where there is an increased risk for getting certain kinds of fungal infections (histoplasmosis, coccidioidomycosis, or blastomycosis). These infections may happen or become more severe if you use Adalimumab-ryvk. Ask your doctor if you do not know if you have lived in an area where these infections are common.
- have or have had hepatitis B.
- use the medicine ORENCIA (abatacept), KINERET (anakinra), RITUXAN (rituximab), IMURAN (azathioprine), or PURINETHOL (6-mercaptopurine, 6-MP).
- are scheduled to have major surgery.

After starting Adalimumab-ryvk, call your doctor right away if you have an infection, or any sign of an infection.

Adalimumab-ryvk can make you more likely to get infections or make any infection that you may have worse.

Cancer

- For children and adults taking Tumor Necrosis Factor (TNF)-blockers, including Adalimumab-ryvk, the chances of getting cancer may increase.
- There have been cases of unusual cancers in children, teenagers, and young adults using TNF-blockers.
- People with rheumatoid arthritis (RA), especially more serious RA, may have a higher chance for getting a kind of cancer called lymphoma.
- If you use TNF blockers including Adalimumab-ryvk, your chance of getting two types of skin cancer may increase (basal cell cancer and squamous cell cancer of the skin). These types of cancer are generally not life-threatening if treated. Tell your doctor if you have a bump or open sore that does not heal.
- Some people receiving TNF blockers including Adalimumab-ryvk developed a rare type of cancer called hepatosplenic T-cell lymphoma. This type of cancer often results in death. Most of these people were male teenagers or young men. Also, most people were being treated for Crohn’s disease or ulcerative colitis with another medicine called IMURAN (azathioprine) or PURINETHOL (6-mercaptopurine, 6-MP).

What is Adalimumab-ryvk?

Adalimumab-ryvk is a medicine called a Tumor Necrosis Factor (TNF) blocker. Adalimumab-ryvk is used:

- To reduce the signs and symptoms of:
  - moderate to severe RA in adults. Adalimumab-ryvk can be used alone, with methotrexate, or with certain other medicines.
  - moderate to severe polyarticular juvenile idiopathic arthritis (JIA) in children 2 years and older. Adalimumab-ryvk can be used alone or with methotrexate.
  - psoriatic arthritis (PsA) in adults. Adalimumab-ryvk can be used alone or with certain other medicines.
  - ankylosing spondylitis (AS) in adults.
  - moderate to severe hidradenitis suppurativa (HS) in people 12 years and older.
- To treat moderate to severe Crohn’s disease (CD) in adults and children 6 years of age and older.
- To treat moderate to severe ulcerative colitis (UC) in adults. It is not known if adalimumab products are effective in people who stopped responding to or could not tolerate TNF-blocker medicines.
- To treat moderate to severe chronic (lasting a long time) plaque psoriasis (Ps) in adults who have the condition in many areas of their body and who may benefit from taking injections or pills (systemic therapy) or phototherapy (treatment using ultraviolet light alone or with pills).
- To treat non-infectious intermediate, posterior, and panuveitis in adults and children 2 years of age and older.

What should I tell my doctor before taking Adalimumab-ryvk?

Adalimumab-ryvk may not be right for you. Before starting Adalimumab-ryvk, tell your doctor about all of your medical conditions, including if you:

- have an infection. See “What is the most important information I should know about Adalimumab-ryvk?”
- have or have had cancer.
- have any numbness or tingling or have a disease that affects your nervous system such as multiple sclerosis or Guillain-Barré syndrome.
- have or had heart failure.
- have recently received or are scheduled to receive a vaccine. You may receive vaccines, except for live vaccines while using Adalimumab-ryvk. Children should be brought up to date with all vaccines before starting Adalimumab-ryvk.
- are allergic to Adalimumab-ryvk or to any of its ingredients. See the end of this Medication Guide for a list of ingredients in Adalimumab-ryvk.
- are pregnant or plan to become pregnant, breastfeeding or plan to breastfeed. You and your doctor should decide if you should take Adalimumab-ryvk while you are pregnant or breastfeeding.
- have a baby and you were using Adalimumab-ryvk during your pregnancy. Tell your baby’s doctor before your baby receives any vaccines.

Tell your doctor about all the medicines you take, including prescription and over-the-counter medicines, vitamins, and herbal supplements.

Especially tell your doctor if you use:

- ORENCIA (abatacept), KINERET (anakinra), REMICADE (infliximab), ENBREL (etanercept), CIMZIA (certolizumab pegol) or SIMPONI (golimumab), because you should not use Adalimumab-ryvk while you are also using one of these medicines.
- RITUXAN (rituximab). Your doctor may not want to give you Adalimumab-ryvk if you have received RITUXAN (rituximab) recently.
- IMURAN (azathioprine) or PURINETHOL (6-mercaptopurine, 6-MP).

Keep a list of your medicines with you to show your doctor and pharmacist each time you get a new medicine.

How should I take Adalimumab-ryvk?

- Adalimumab-ryvk is given by an injection under the skin. Your doctor will tell you how often to take an injection of Adalimumab-ryvk. This is based on your condition to be treated. Do not inject Adalimumab-ryvk more often than you were prescribed.
- See the Instructions for Use inside the carton for complete instructions for the right way to prepare and inject Adalimumab-ryvk.
- Make sure you have been shown how to inject Adalimumab-ryvk before you do it yourself. You can call your doctor or 1-877-605-7243 if you have any questions about giving yourself an injection. Someone you know can also help you with your injection after they have been shown how to prepare and inject Adalimumab-ryvk.
- Do not try to inject Adalimumab-ryvk yourself until you have been shown the right way to give the injections. If your doctor decides that you or a caregiver may be able to give your injections of Adalimumab-ryvk at home, you should receive training on the right way to prepare and inject Adalimumab-ryvk.
- Do not miss any doses of Adalimumab-ryvk unless your doctor says it is okay. If you forget to take Adalimumab-ryvk, inject a dose as soon as you remember. Then, take your next dose at your regular scheduled time. This will put you back on schedule. In case you are not sure when to inject Adalimumab-ryvk, call your doctor or pharmacist.
- If you take more Adalimumab-ryvk than you were told to take, call your doctor.

What are the possible side effects of Adalimumab-ryvk?

Adalimumab-ryvk can cause serious side effects, including:

See “What is the most important information I should know about Adalimumab-ryvk?”

- Serious Infections.

Your doctor will examine you for TB and perform a test to see if you have TB. If your doctor feels that you are at risk for TB, you may be treated with medicine for TB before you begin treatment with Adalimumab-ryvk and during treatment with Adalimumab-ryvk. Even if your TB test is negative your doctor should carefully monitor you for TB infections while you are taking Adalimumab-ryvk. People who had a negative TB skin test before receiving adalimumab products have developed active TB. Tell your doctor if you have any of the following symptoms while taking or after taking Adalimumab-ryvk:

- cough that does not go away
- low grade fever

- weight loss
- loss of body fat and muscle (wasting)

- Hepatitis B infection in people who carry the virus in their blood.

If you are a carrier of the hepatitis B virus (a virus that affects the liver), the virus can become active while you use Adalimumab-ryvk. Your doctor should do blood tests before you start treatment, while you are using Adalimumab-ryvk, and for several months after you stop treatment with Adalimumab-ryvk. Tell your doctor if you have any of the following symptoms of a possible hepatitis B infection:

- muscle aches
- feel very tired
- dark urine
- skin or eyes look yellow
- little or no appetite
- vomiting

- clay-colored bowel movements
- fever
- chills
- stomach discomfort
- skin rash

- Allergic reactions. Allergic reactions can happen in people who use Adalimumab-ryvk. Call your doctor or get medical help right away if you have any of these symptoms of a serious allergic reaction:

- hives
- trouble breathing

- swelling of your face, eyes, lips, or mouth

- Nervous system problems. Signs and symptoms of a nervous system problem include: numbness or tingling, problems with your vision, weakness in your arms or legs, and dizziness.
- Blood problems. Your body may not make enough of the blood cells that help fight infections or help to stop bleeding. Symptoms include a fever that does not go away, bruising or bleeding very easily, or looking very pale.
- New heart failure or worsening of heart failure you already have. Call your doctor right away if you get new or worsening symptoms of heart failure while taking Adalimumab-ryvk, including:

- shortness of breath
- sudden weight gain

- swelling of your ankles or feet

- Immune reactions including a lupus-like syndrome. Symptoms include chest discomfort or pain that does not go away, shortness of breath, joint pain, or a rash on your cheeks or arms that gets worse in the sun. Symptoms may improve when you stop Adalimumab-ryvk.
- Liver problems. Liver problems can happen in people who use TNF-blocker medicines. These problems can lead to liver failure and death. Call your doctor right away if you have any of these symptoms:

- feel very tired
- poor appetite or vomiting

- skin or eyes look yellow
- pain on the right side of your stomach (abdomen)

- Psoriasis. Some people using adalimumab products had new psoriasis or worsening of psoriasis they already had. Tell your doctor if you develop red scaly patches or raised bumps that are filled with pus. Your doctor may decide to stop your treatment with Adalimumab-ryvk.

Call your doctor or get medical care right away if you develop any of the above symptoms. Your treatment with Adalimumab-ryvk may be stopped.

The most common side effects of Adalimumab-ryvk include:

- injection site reactions: redness, rash, swelling, itching, or bruising. These symptoms usually will go away within a few days. Call your doctor right away if you have pain, redness or swelling around the injection site that does not go away within a few days or gets worse.
- upper respiratory infections (including sinus infections).
- headaches.
- rash.

These are not all the possible side effects with Adalimumab-ryvk. Tell your doctor if you have any side effect that bothers you or that does not go away. Ask your doctor or pharmacist for more information.

Call your doctor for medical advice about side effects. You may report side effects to FDA at 1-800-FDA-1088.

How should I store Adalimumab-ryvk?

- Store Adalimumab-ryvk in the refrigerator at 36°F to 46°F (2°C to 8°C). Store Adalimumab-ryvk in the original carton until use to protect it from light.
- Do not freeze Adalimumab-ryvk. Do not use Adalimumab-ryvk if frozen, even if it has been thawed.
- Refrigerated Adalimumab-ryvk may be used until the expiration date printed on the Adalimumab-ryvk carton, dose tray, autoinjector or prefilled syringe. Do not use Adalimumab-ryvk after the expiration date.
- If needed, for example when you are traveling, you may also store Adalimumab-ryvk at room temperature up to
  77°F (25°C) for up to 30 days. Store Adalimumab-ryvk in the original carton until use to protect it from light.
- Throw away Adalimumab-ryvk if it has been kept at room temperature and not been used within 30 days.
- Record the date you first remove Adalimumab-ryvk from the refrigerator on the carton and dose tray.
- Do not store Adalimumab-ryvk in extreme heat or cold.
- Do not use Adalimumab-ryvk if the liquid is cloudy, discolored, or has flakes or particles in it.
- Do not drop or crush Adalimumab-ryvk. The prefilled syringe is glass.

Keep Adalimumab-ryvk, injection supplies, and all other medicines out of the reach of children.

General information about the safe and effective use of Adalimumab-ryvk.

Medicines are sometimes prescribed for purposes other than those listed in a Medication Guide. Do not use Adalimumab-ryvk for a condition for which it was not prescribed. Do not give Adalimumab-ryvk to other people, even if they have the same condition. It may harm them. This Medication Guide summarizes the most important information about Adalimumab-ryvk. If you would like more information, talk with your doctor. You can ask your pharmacist or doctor for information about Adalimumab-ryvk that is written for health professionals.

What are the ingredients in Adalimumab-ryvk?
Active ingredient: adalimumab-ryvk.
Inactive ingredients: polysorbate 80, sodium chloride, sucrose, and Water for Injection. Sodium hydroxide and hydrochloric acid are added as necessary to adjust pH.

Brands listed are the trademarks of their respective owners.

Manufactured By: Alvotech USA Inc., Leesburg, VA 20175
U.S. License No. 2225

Manufactured At: Alvotech Hf, Reykjavik, 102

Product of Iceland

Manufactured For: Quallent Pharmaceuticals Health LLC, Grand Cayman, Cayman Islands

For more information call 1-877-605-7243.

This Medication Guide has been approved by the U.S. Food and Drug Administration. Revised: 10/2025

IFU AI

INSTRUCTIONS FOR USE

Adalimumab-ryvk (ada-LIM-u-mab ryvk)

injection, for subcutaneous use

40 mg/0.4 mL

Single-Dose Autoinjector

Before Injecting: Your healthcare provider should show you how to use Adalimumab-ryvk before you use it for the first time. Call your healthcare provider or 1-877-605-7243 if you have any questions.

Adalimumab-ryvk Autoinjector Parts

Important Information You Need to Know Before Injecting Adalimumab-ryvk

Do not use the Autoinjector and call your healthcare provider or pharmacist if:

- Liquid is cloudy, discolored, or has flakes or particles in it
- Expiration date has passed

- Liquid has been frozen (even if thawed) or left in direct sunlight
- The Autoinjector has been dropped or crushed

Keep the Clear Cap on until right before your injection.
How should I store Adalimumab-ryvk?

- Store Adalimumab-ryvk in the refrigerator between
  36°F to 46°F (2°C to 8°C).
- Store Adalimumab-ryvk in the original carton until use to protect it from light.
- Do not freeze.
- Refrigerated Adalimumab-ryvk may be used until the expiration date printed on the Adalimumab-ryvk carton, dose tray or Autoinjector.
- If needed, for example when you are traveling, you may also store Adalimumab-ryvk at room temperature up to 77°F (25°C) for up to 30 days.

- Throw away Adalimumab-ryvk if it has been kept at room temperature and not used within 30 days.
- Record the date you first remove Adalimumab-ryvk from the refrigerator in the spaces provided on the carton and dose tray.
- Do not store Adalimumab-ryvk in extreme heat or cold.
- Do not drop or crush Adalimumab-ryvk. The prefilled syringe is glass.

Keep Adalimumab-ryvk, injection supplies, and all other medicines out of reach of children.

Read Instructions on All Pages Before Using the Adalimumab-ryvk Autoinjector

Step 1

Take Adalimumab-ryvk out of the refrigerator (see Figure A).

Leave Adalimumab-ryvk at room temperature for 15 to 30 minutes before injecting (see Figure B).

- Do not remove the Clear Cap while allowing Adalimumab-ryvk to reach room temperature.
- Do not warm Adalimumab-ryvk in any other way. For example, do not warm it in a microwave or in hot water.
- Do not use the Autoinjector if liquid has been frozen (even if thawed).

Step 2

Check expiration date on the Autoinjector label (see Figure C). Do not use the Autoinjector if expiration date has passed.

Place the following on a clean, flat surface (see Figure D):

- 1 single-dose Autoinjector and alcohol swab
- 1 cotton ball or gauze pad (not included)
- Puncture-resistant sharps disposal container (not included). See Step 9 at the end of this Instructions for Use for instructions on how to throw away (dispose of) your Adalimumab-ryvk Autoinjector

Wash and dry your hands (see Figure E).

Step 3

Choose an injection site (see Figure F):

- On the front of your thighs or
- Your abdomen (belly) at least 2 inches from your navel (belly button)
- Different from your last injection site
  Wipe the injection site in a circular motion with the alcohol swab (see Figure G).

Do not inject through clothes

- Do not inject into skin that is sore, bruised, red, hard, scarred, has stretch marks, or areas with psoriasis plaques

Step 4

Hold the Autoinjector with the Gray Body Grip Area facing up.

Check the window (see Figure H).

- It is normal to see different plunger stopper position, from about halfway down to higher up in the inspection window.
- It is normal to see 1 or more bubbles in the window
- Make sure the liquid is clear and colorless
- Do not use the Autoinjector if the liquid is cloudy, discolored, or has flakes or particles in it
- Do not use the Autoinjector if it has been dropped or crushed

Step 5

Pull the Clear Cap straight off of the Autoinjector
(see Figure I).

Throw the Clear Cap away.

- It is normal to see a few drops of liquid come out of the needle
- Never put the clear cap back on. It may damage the needle.

Turn the Autoinjector so that the orange needle sleeve points toward the injection site.

Step 6

Squeeze the skin at your injection site to make a raised area and hold it firmly until the injection is complete.

Place the orange needle sleeve straight (90° angle) against the injection site (see Figure J).

Hold the Autoinjector so that you can see the window.

Step 7

It is important that you firmly push the Autoinjector down all the way against the injection site.

Keep pushing the Autoinjector down during the injection (see Figure K).

- The first “click” will signal the start of the injection (see Figure K). It may take up to
  10 seconds after the first ‘click’ to complete.

- Injection is complete when the orange indicator has stopped moving and you hear a second ‘click’ (see Figure L). Do not lift up or let go of the pressure from the injection site, until you have confirmed the injection is complete.

Step 8

When the injection is completed, slowly pull the Autoinjector from the skin. The orange needle sleeve will cover the needle tip (see Figure M).

- A small amount of liquid on the injection site is normal

If there are more than a few drops of liquid on the injection site, call 1-877-605-7243 for help.

After completing the injection, place a cotton ball or gauze pad on the skin of the injection site.

- Do not rub
- Slight bleeding at the injection site is normal

Step 9

- Put your used Autoinjectors in a FDA-cleared sharps disposal container right away after use (see figure N). Do not throw away (dispose of) the Autoinjector in the household trash.
- If you do not have a FDA-cleared sharps disposal container, you may use a household container that is:
  - made of a heavy-duty plastic,
  - can be closed with a tight-fitting, puncture-resistant lid, without sharps being able to come out,
  - upright and stable during use,
  - leak-resistant, and
  - properly labeled to warn of hazardous waste inside the container.
- When your sharps disposal container is almost full, you will need to follow your community guidelines for the right way to dispose of your sharps disposal container. There may be state or local laws about how you should throw away used needles and syringes. For more information about safe sharps disposal, and for specific information about sharps disposal in the state that you live in, go to the FDA’s website at: http://www.fda.gov/safesharpsdisposal.
- Do not dispose of your used sharps disposal container in your household trash unless your community guidelines permit this. Do not recycle your used sharps disposal container.

The Clear Cap, alcohol swab, cotton ball or gauze pad, dose tray, and packaging may be placed in your household trash.

Questions About Using the Adalimumab-ryvk Autoinjector

What if I have not received in person training from a healthcare provider?

- Call your healthcare provider or visit www.quallentpharmaceuticals.com if you need help

How do I know when the injection is complete?

- The orange indicator has stopped moving and you hear a second ‘click’. This takes up to 10 seconds.

What should I do if there are more than a few drops of liquid on the injection site?

- Call 1-877-605-7243 for help
  What if I do not have an FDA-cleared sharps disposal container or proper household container?
- If you do not have a FDA-cleared sharps disposal container, you may use a household container that is made of a heavy-duty plastic, can be closed with a tight-fitting and puncture-resistant lid without sharps being able to come out, upright and stable during use, leak-resistant, and properly labeled to warn of hazardous waste inside the container.

Always keep the Autoinjector and the sharps disposal container out of reach of children.

Keep a record of the dates and locations of your injections. To help remember when to take Adalimumab-ryvk, mark your calendar ahead of time.

Manufactured By: Alvotech USA Inc.,Leesburg, VA 20175

U.S. License No. 2225

Manufactured At: Alvotech Hf, Reykjavik, 102

Product of Iceland

Manufactured For: Quallent Pharmaceuticals Health LLC, Grand Cayman, Cayman Islands

This Instructions for Use has been approved by the U.S. Food and Drug Administration. Revised 11/2025

IFU PFS

INSTRUCTIONS FOR USE

Adalimumab-ryvk (ada-LIM-u-mab ryvk)

injection, for subcutaneous use

Single-Dose Prefilled Syringe

Before Injecting: Your healthcare provider should show you how to use Adalimumab-ryvk before you use it for the first time. Call your healthcare provider or 1-877-605-7243 if you need help.

Adalimumab-ryvk Single-Dose Prefilled Syringe Parts

Important Information You Need to Know Before Injecting Adalimumab-ryvk

Do not use the prefilled syringe and call your healthcare provider or pharmacist if:

- Liquid is cloudy, discolored, or has flakes or particles in it
- Expiration date has passed

- Liquid has been frozen (even if thawed) or left in direct sunlight
- The prefilled syringe has been dropped or crushed

Keep the needle cover on until right before your injection.

How should I store Adalimumab-ryvk?

- Store Adalimumab-ryvk in the refrigerator between
  36°F to 46°F (2°C to 8°C).
- Store Adalimumab-ryvk in the original carton until use to protect it from light.
- Do not freeze.
- Refrigerated Adalimumab-ryvk may be used until the expiration date printed on the Adalimumab-ryvk carton, dose tray or prefilled syringe.
- If needed, for example when you are traveling, you may also store Adalimumab-ryvk at room temperature up to 77°F (25°C) for up to 30 days.

- Throw away Adalimumab-ryvk if it has been kept at room temperature and not used within 30 days.
- Record the date you first remove Adalimumab-ryvk from the refrigerator in the spaces provided on the carton and dose tray.
- Do not store Adalimumab-ryvk in extreme heat or cold.

Keep Adalimumab-ryvk, injection supplies, and all other medicines out of reach of children.

Read Instructions on All Pages Before Using the Adalimumab-ryvk Prefilled Syringe

Step 1

Take Adalimumab-ryvk out of the refrigerator (see Figure A).

Leave Adalimumab-ryvk at room temperature for
15 to 30 minutes before injecting (see Figure B).

- Do not remove the needle cover while allowing Adalimumab-ryvk to reach room temperature.
- Do not warm Adalimumab-ryvk in any other way. For example, do not warm it in a microwave or in hot water.
- Do not use the prefilled syringe if liquid has been frozen (even if thawed).

Step 2

Figure C

Check expiration date on the prefilled syringe label (see Figure C).

- Do not use the prefilled syringe if expiration date has passed.

Check the liquid drug in the syringe to ensure it is clear and colorless (see Figure C).

- Do not use the syringe and call your healthcare provider or pharmacist if: Liquid is cloudy, discolored, or has flakes or particles in it.

Step 3

Figure D

Place the following on a clean, flat surface (see Figure D):

- 1 single-dose prefilled syringe and alcohol swab
- 1 cotton ball or gauze pad (not included)
- Puncture-resistant sharps disposal container (not included). See Step 9 at the end of this Instructions for Use for instructions on how to throw away (dispose of) your prefilled syringe

Wash and dry your hands (see Figure E).

Step 4

Figure F

Choose an injection site (see Figure F):

- On the front of your thighs or
- Your abdomen (belly) at least 2 inches from your navel (belly button)
- Different from your last injection site
- Wipe the injection site in a circular motion with the alcohol swab (see Figure F)
- Do not inject through clothes
- Do not inject into skin that is sore, bruised, red, hard, scarred, has stretch marks, or areas with psoriasis plaques

Step 5

Figure G

Hold the prefilled syringe in one hand (see Figure G).

Gently pull the needle cover straight off with the other hand.

- Throw the needle cover away
- Do not recap
- Do not touch the needle with your fingers or let the needle touch anything
- You may see a drop of liquid at the end of the needle. This is normal.

Step 6

Figure H

Hold the body of the prefilled syringe in one hand between the thumb and index fingers. Hold the prefilled syringe in your hand like a pencil (see Figure H).

Do not pull back on the plunger at any time.

Gently squeeze the area of cleaned skin at your injection site with your other hand. Hold the skin firmly (see Figure H).

Step 7

Figure I

Figure J

Insert the needle into the skin at about a 45-degree angle using a quick, dart-like motion (see Figure I).

- After the needle is in, let go of the skin.

Slowly push the plunger all the way in until all of the liquid is injected and the prefilled syringe is empty (see Figure J).

Step 8

Figure K

When the injection is completed, slowly lift your finger from the plunger. This will let the empty syringe move up until the entire needle is covered by the needle guard (see Figure K).

- The needle will not retract unless all the liquid is injected. Speak to your doctor, pharmacist or nurse if you think you have not given a full dose.
- It is normal to see a spring around the plunger rod after the needle is retracted.

After completing the injection, place a cotton ball or gauze pad on the skin of the injection site.

- Do not rub
- Slight bleeding at the injection site is normal

Step 9

Figure L

How should I dispose of the used Adalimumab-ryvk prefilled syringe?

- Put your used syringes in a FDA-cleared sharps disposal container right away after use. Do not throw away (dispose of) syringes in the household trash (see Figure L).
  - If you do not have a FDA-cleared sharps disposal container, you may use a household container that is:
    - made of a heavy-duty plastic,
    - can be closed with a tight-fitting, puncture-resistant lid, without sharps being able to come out,
    - upright and stable during use,
    - leak-resistant, and
    - properly labeled to warn of hazardous waste inside the container.
- When your sharps disposal container is almost full, you will need to follow your community guidelines for the right way to dispose of your sharps disposal container. There may be state or local laws about how you should throw away used syringes. For more information about safe sharps disposal, and for specific information about sharps disposal in the state that you live in, go to the FDA’s website at: http://www.fda.gov/safesharpsdisposal.
- Do not dispose of your used sharps disposal container in your household trash unless your community guidelines permit this. Do not recycle your used sharps disposal container.

The needle cover, alcohol swab, cotton ball or gauze pad, dose tray, and packaging may be placed in your household trash.

Questions About Using the Adalimumab-ryvk Single-Dose Prefilled Syringe

What if I have not received in-person training from a healthcare provider?

- Call your healthcare provider or visit www.quallentpharmaceuticals.com if you need help

What if I do not have an FDA-cleared sharps disposal container or proper household container?

- Call 1-800-448-6472 for a free FDA-cleared sharps disposal container.

Always keep the prefilled syringe and the sharps disposal container out of the reach of children.

Keep a record of the dates and locations of your injections. To help remember when to take Adalimumab-ryvk, mark your calendar ahead of time.

Manufactured By: Alvotech USA Inc., Leesburg, VA 20175

U.S. License No. 2225

Manufactured At: Alvotech Hf, Reykjavik, 102

Product of Iceland

Manufactured For: Quallent Pharmaceuticals Health LLC, Grand Cayman, Cayman Islands

This Instructions for Use has been approved by the U.S. Food and Drug Administration. Revised: 6/2024

PACKAGE LABEL.PRINCIPAL DISPLAY PANEL

NDC 82009-156-22

Adalimumab-ryvk
Injection

40 mg/0.4 mL

For Subcutaneous Use Only
2 Single-Dose Autoinjectors

Rx Only

This carton contains:
- 2 Dose Trays (each containing 1 single-dose Autoinjector with 29 gauge 1/2 inch length fixed needle)
- 2 Alcohol preps
- 1Quick Reference Guide
- 1 Instructions For Use
- 1 Medication Guide
- 1 Prescribing Information

PACKAGE LABEL.PRINCIPAL DISPLAY PANEL PFS

NDC 82009-158-22

Adalimumab-ryvk
Injection

40 mg/0.4 mL

For Subcutaneous Use Only
2 Single-Dose Prefilled Syringes

Rx Only

This carton contains:
- 2 Dose Trays (each containing 1 single-dose prefilled syringe)
- 2 Alcohol preps
- 1Quick Reference Guide
- 1 Instructions For Use
- 1 Medication Guide
- 1 Prescribing Information